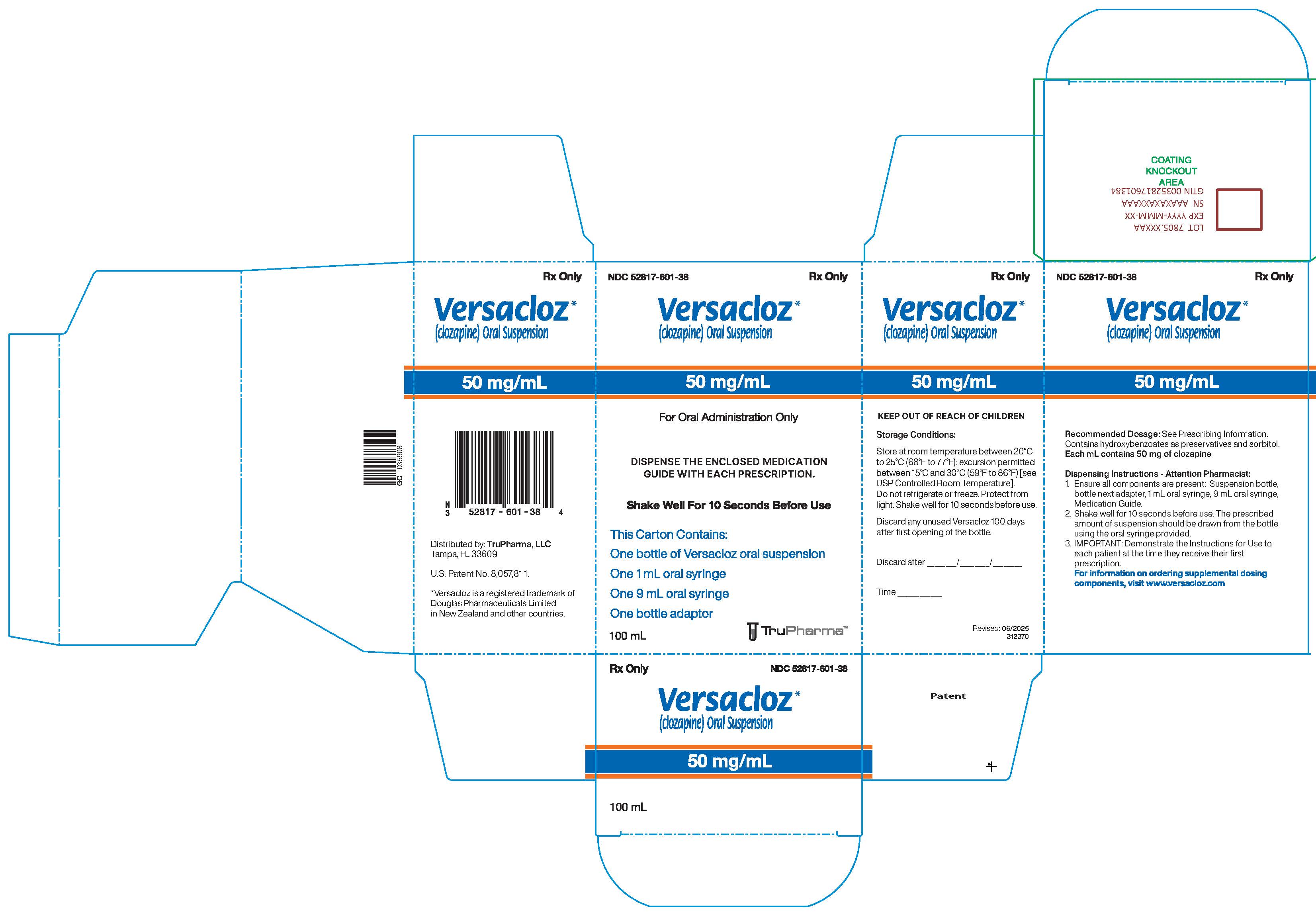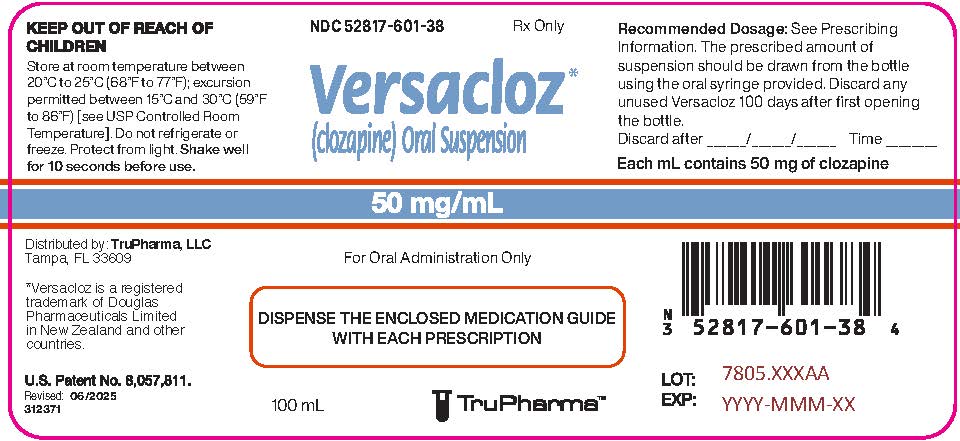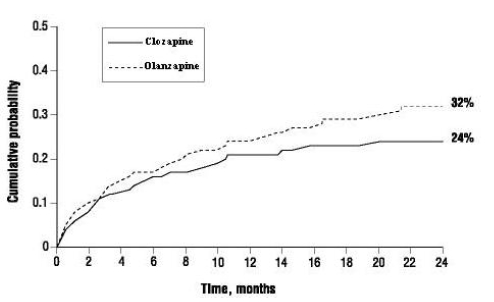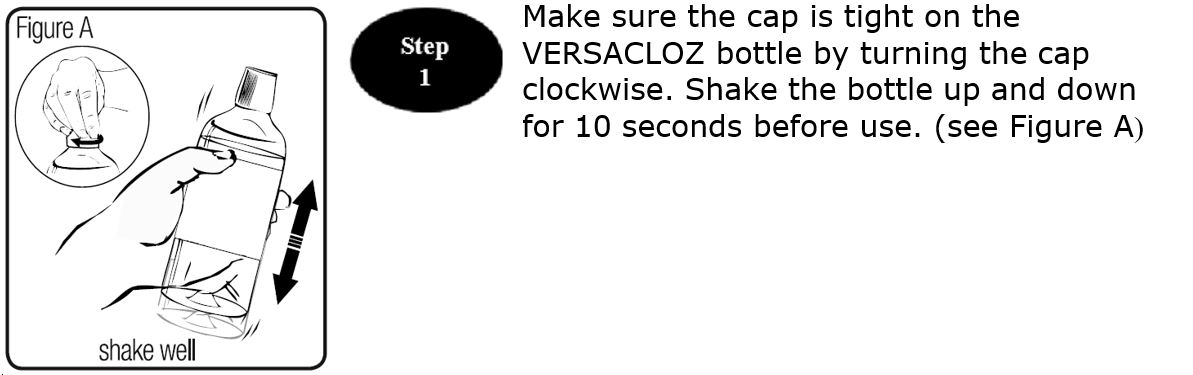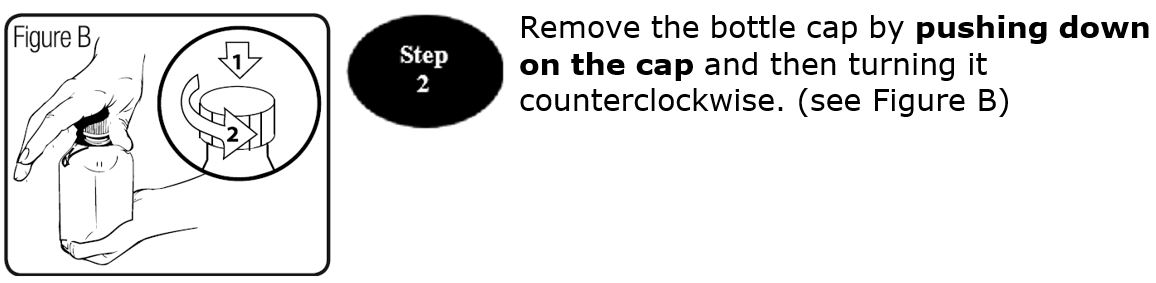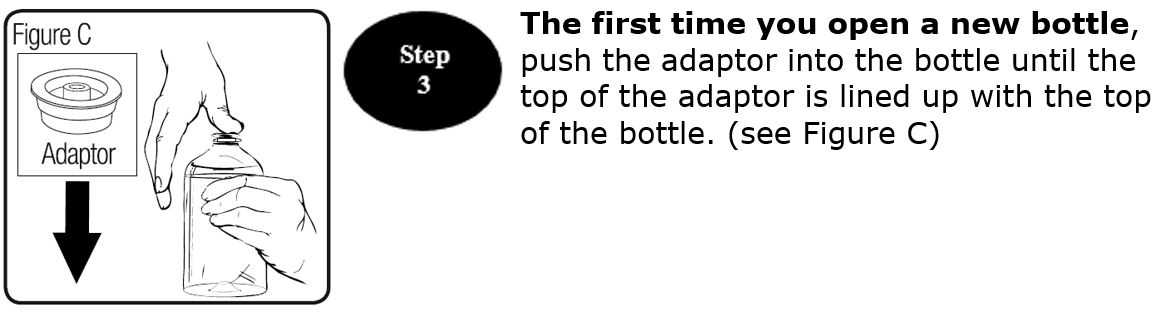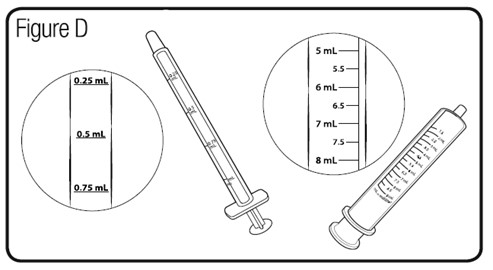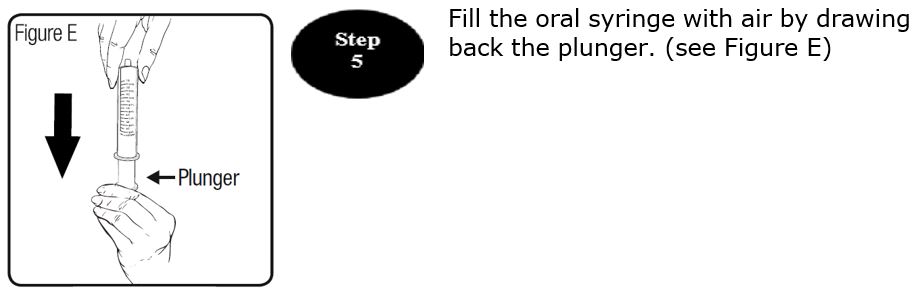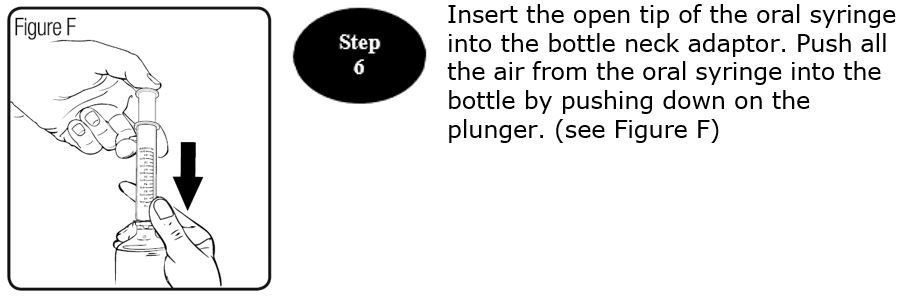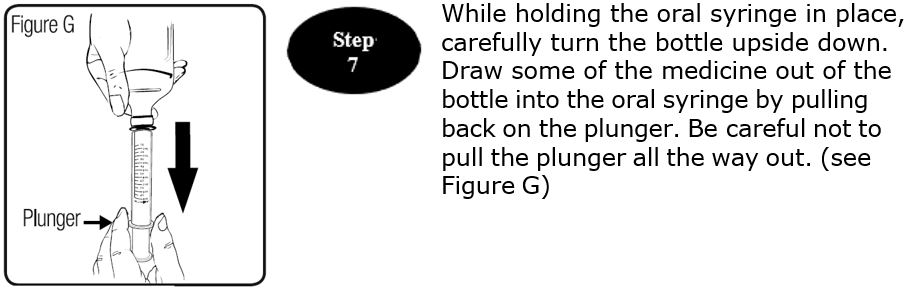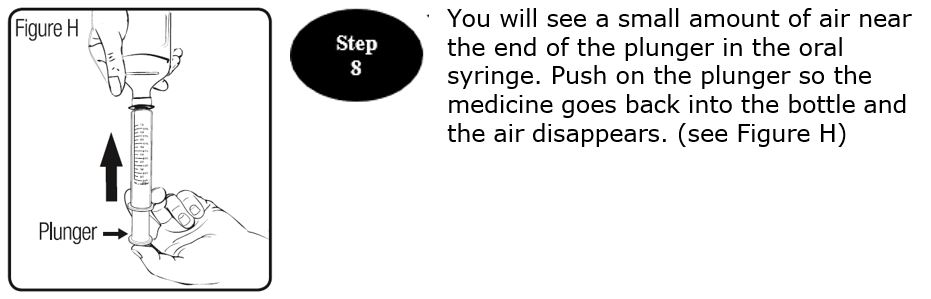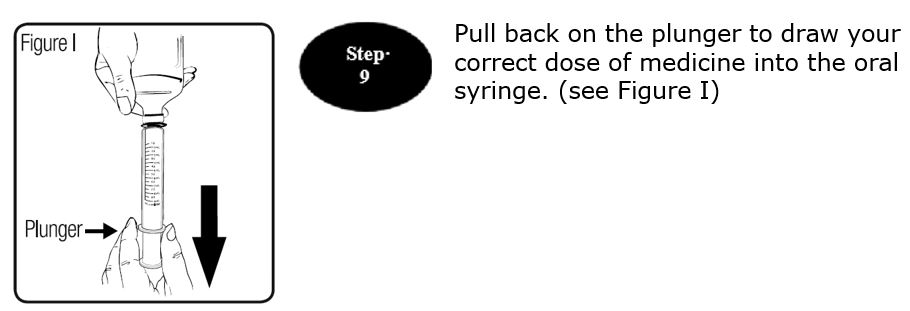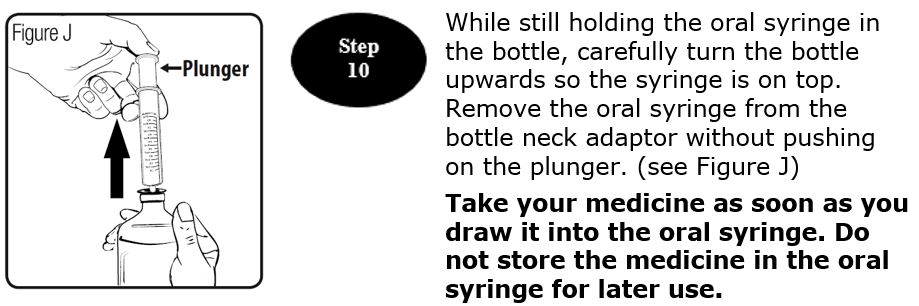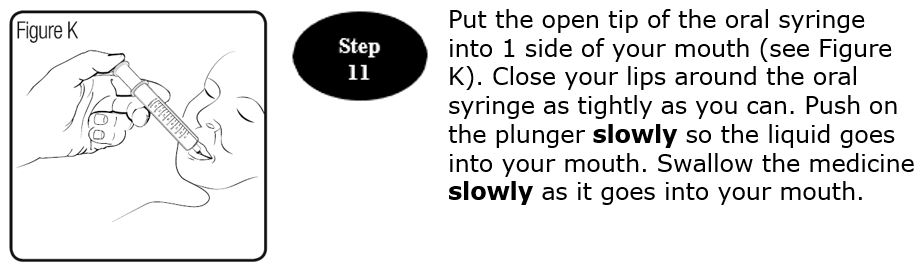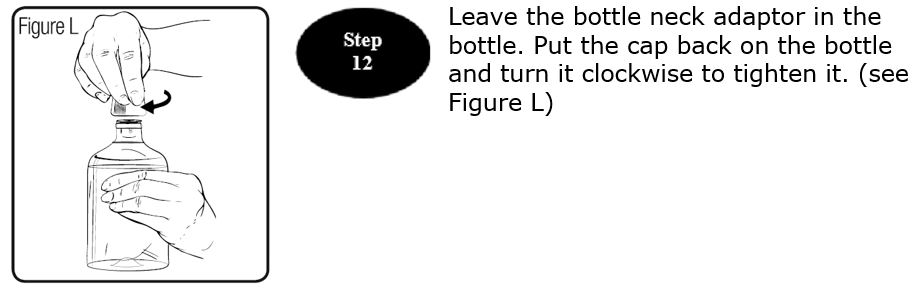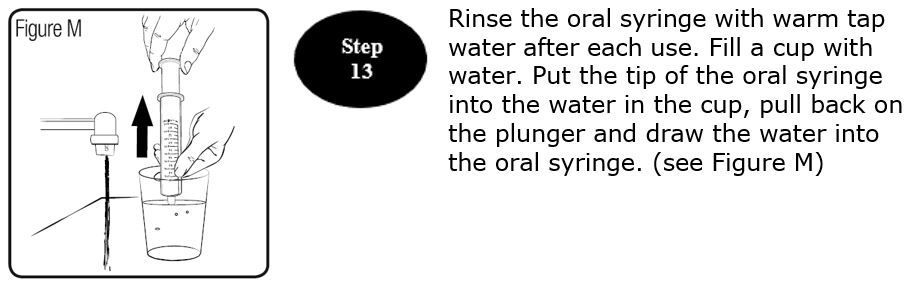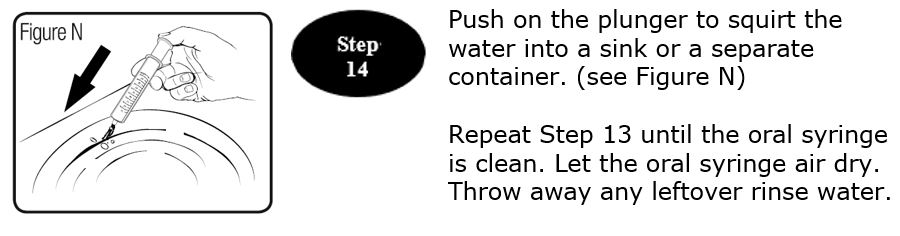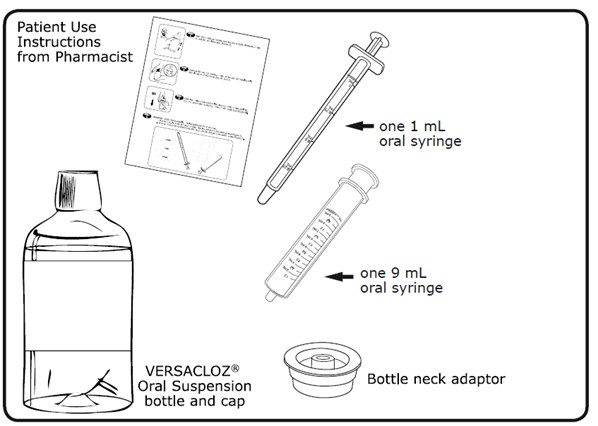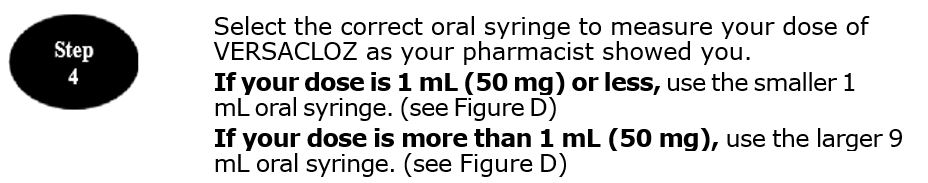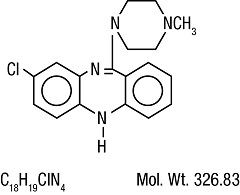 DRUG LABEL: VERSACLOZ
NDC: 52817-601 | Form: SUSPENSION
Manufacturer: TruPharma LLC
Category: prescription | Type: HUMAN PRESCRIPTION DRUG LABEL
Date: 20250623

ACTIVE INGREDIENTS: CLOZAPINE 50 mg/1 mL
INACTIVE INGREDIENTS: GLYCERIN; SORBITOL; SODIUM PHOSPHATE, MONOBASIC, DIHYDRATE; XANTHAN GUM; METHYLPARABEN SODIUM; PROPYLPARABEN SODIUM; WATER; SODIUM HYDROXIDE; POVIDONE

HIGHLIGHTS OF PRESCRIBING INFORMATION

These highlights do not include all the information needed to use VERSACLOZ®safely and effectively. See full prescribing information for VERSACLOZ®.
VERSACLOZ (clozapine) oral suspension
Initial U.S. Approval: 1989

RECENT MAJOR CHANGES

Boxed Warning 6/2025

Indications and Usage 6/2025

Dosage and Administration (2.1, 2.2, 2.3, 2.4, 2.5, 2.6, 2.7, 2.8, 2.9) 6/2025

Warnings and Precautions (5.1) 6/2025

WARNING: SEVERE NEUTROPENIA; ORTHOSTATIC HYPOTENSION, BRADYCARDIA, AND SYNCOPE; SEIZURE; MYOCARDITIS, PERICARDITIS, AND CARDIOMYOPATHY; INCREASED MORTALITY IN ELDERLY PATIENTS WITH DEMENTIA-RELATED PSYCHOSIS

See full prescribing information for complete boxed warning.

- Severe Neutropenia: Clozapine can cause severe neutropenia, which can lead to serious and fatal infections. Patients initiating and continuing treatment with VERSACLOZ must have a baseline blood absolute neutrophil count (ANC) measured before treatment initiation and regular ANC monitoring during treatment (2.1, 5.1).
- VERSACLOZ is available only through a restricted program called the Clozapine REMS (5.2).
- Orthostatic Hypotension, Bradycardia, and Syncope: Risk is dose-related. Starting dose is 12.5 mg. Titrate gradually and use divided dosages (2.2, 2.6, 5.3).
- Seizure: Risk is dose-related. Titrate gradually and use divided doses. Use with caution in patients with history of seizure or risk factors for seizure (2.2, 5.5).
- Myocarditis, Pericarditis, Cardiomyopathy and Mitral Valve Incompetence: Can be fatal. Discontinue and obtain cardiac evaluation if findings suggest these cardiac reactions (5.6).
- Increased Mortality in Elderly Patients with Dementia-Related Psychosis: VERSACLOZ is not approved for this condition (5.7).

1 INDICATIONS AND USAGE

VERSACLOZ is an atypical antipsychotic indicated for:

- Treatment of severely ill patients with schizophrenia who fail to respond adequately to standard antipsychotic treatment. Because of the risks of severe neutropenia and of seizure associated with its use, VERSACLOZ should be used only in patients who have failed to respond adequately to standard antipsychotic treatment (1.1).
- Reducing the risk of recurrent suicidal behavior in patients with schizophrenia or schizoaffective disorder who are judged to be at chronic risk for re-experiencing suicidal behavior (1.2).

2 DOSAGE AND ADMINISTRATION

- Recommended starting oral dosage is 12.5 mg once daily or twice daily (2.2).
- If well-tolerated, increase the total daily dosage in increments of 25 mg to 50 mg per day to achieve a target dosage of 150 mg to 225 mg twice per day by the end of two weeks (2.2).
- Subsequently may increase the dosage in increments up to 100 mg once or twice weekly (2.2).
- Maximum daily dosage is 450 mg twice daily (2.2).
- Administer with or without food. See important administration instructions in the full prescribing information (2.3).
- See the dosage modifications based on ANC results and recommended frequency of ANC testing in the full prescribing information (2.4, 2.5).
- See recommendations for discontinuing VERSACLOZ treatment (2.6), restarting VERSACLOZ after interrupting dosing (2.7), dosage modifications for drug interactions (2.8), dosage recommendations in patients with renal or hepatic impairment and CYP2D6 poor metabolizers (2.9) in the full prescribing information.

3 DOSAGE FORMS AND STRENGTHS

Oral suspension: 50 mg per mL (3).

4 CONTRAINDICATIONS

- Known hypersensitivity to clozapine or any other component of VERSACLOZ (4).

5 WARNINGS AND PRECAUTIONS

- Severe neutropenia:See Boxed Warning (5.1)
- Gastrointestinal Hypomotility with Severe Complications:Severe gastrointestinal adverse reactions have occurred with the use of VERSACLOZ. If constipation is identified, close monitoring and prompt treatment is advised (5.8).
- Eosinophilia:Assess for organ involvement (e.g., myocarditis, pancreatitis, hepatitis, colitis, nephritis). Discontinue if these occur (5.9).
- QT Interval Prolongation:Can be fatal. Consider additional risk factors for prolonged QT interval (disorders and drugs) (5.10).
- Metabolic Changes:Atypical antipsychotic drugs have been associated with metabolic changes that may increase cardiovascular/cerebrovascular risk. These metabolic changes include:
  - Hyperglycemia and Diabetes Mellitus:Monitor for symptoms of hyperglycemia including polydipsia, polyuria, polyphagia, and weakness. Monitor glucose regularly in patients with diabetes or at risk for diabetes (5.11).
  - Dyslipidemia: Undesirable alterations in lipids have occurred in patients treated with atypical antipsychotics (5.11).
  - Weight Gain:Significant weight gain has occurred. Monitor weight gain (5.11).
- Neuroleptic Malignant Syndrome (NMS):Immediately discontinue and monitor closely. Assess for co-morbid conditions (5.12).
- Hepatotoxicity:Can be fatal. Monitor for hepatotoxicity. Discontinue treatment if hepatitis or transaminase elevations combined with other symptoms occur (5.13).
- Fever:Evaluate for infection, and for neutropenia, NMS (5.14).
- Pulmonary Embolism (PE):Consider PE if respiratory distress, chest, pain, or deep vein thrombosis occurs (5.15).
- Anticholinergic Toxicity:When possible, avoid use with other anticholinergic drugs and use with caution in patients with a current diagnosis or prior history of constipation, urinary retention, clinically significant prostatic hypertrophy, or other conditions in which anticholinergic effects can lead to significant adverse reactions (5.16, 7.1).
- Interference with Cognitive and Motor Performance:Advise caution when operating machinery, including automobiles (5.17).

6 ADVERSE REACTIONS

Most common adverse reactions (≥5%) were: CNS reactions (sedation, dizziness/vertigo, headache, and tremor); cardiovascular reactions (tachycardia, hypotension, and syncope); autonomic nervous system reactions (hypersalivation, sweating, dry mouth, and visual disturbances); gastrointestinal reactions (constipation and nausea); and fever (6.1).

To report SUSPECTED ADVERSE REACTIONS, contact TruPharma, LLC, at 1-877-541-5504 or FDA at 1-800-FDA-1088 or www.fda.gov/medwatch.

7 DRUG INTERACTIONS

- Concomitant use of Strong CYP1A2 Inhibitors: Reduce VERSACLOZ dose to one third when coadministered with strong CYP1A2 inhibitors (e.g., fluvoxamine, ciprofloxacin, enoxacin) (2.7, 7.1).
- Concomitant use of Strong CYP3A4 Inducersis not recommended (2.7, 7.1).
- Discontinuation of CYP1A2 or CYP3A4 Inducers: Consider reducing VERSACLOZ dose when CYP1A2 (e.g., tobacco smoke) or CYP3A4 inducers (e.g., carbamazepine) are discontinued (2.7, 7.1).
- Anticholinergic drugs:Concomitant use may increase the risk for anticholinergic toxicity (5.8, 5.16, 7.1).

8 USE IN SPECIFIC POPULATIONS

- Pregnancy:May cause extrapyramidal and/or withdrawal symptoms in neonates with third trimester exposure (8.1).

FULL PRESCRIBING INFORMATION

WARNING: SEVERE NEUTROPENIA; ORTHOSTATIC HYPOTENSION, BRADYCARDIA, AND SYNCOPE; SEIZURE; MYOCARDITIS, PERICARDITIS, AND CARDIOMYOPATHY; INCREASED MORTALITY IN ELDERLY PATIENTS WITH DEMENTIA-RELATED PSYCHOSIS

Severe Neutropenia

VERSACLOZ has caused severe neutropenia which is associated with an increased risk of serious and potentially fatal infections. Prior to initiating VERSACLOZ treatment, obtain baseline ANC(s). VERSACLOZ initiation is not recommended in patients with a baseline ANC less than 1500/µL (less than 1000/µL for those with Benign Ethnic Neutropenia (also known as Duffy-null associated neutrophil count)). See recommendations for dosage modifications based on ANC levels during VERSACLOZ treatment [see Dosage and Administration (2.4, 2.5)]. Consider a hematology consultation before initiating VERSACLOZ or during VERSACLOZ treatment [see Warnings ad Precautions (5.1)].

Orthostatic Hypotension, Bradycardia, Syncope

Orthostatic hypotension, bradycardia, syncope, and cardiac arrest have occurred with clozapine treatment. The risk is highest during the initial titration period, particularly with rapid dose escalation. These reactions can occur with the first dose, with doses as low as 12.5 mg per day, or when restarting patients who have had even a brief interruption in treatment with Versacloz. Initiate treatment at 12.5 mg once or twice daily; titrate slowly; and use divided dosages to minimize risk. Use VERSACLOZ cautiously in patients with cardiovascular or cerebrovascular disease or conditions predisposing to hypotension (e.g., dehydration, use of antihypertensive medications) [see Dosage and Administration (2.2, 2.7), Warnings and Precautions (5.2)].

Seizures

Seizures have occurred with clozapine treatment. The risk is dose-related. Initiate treatment at 12.5 mg, titrate gradually, and use divided dosing. Use caution when administering VERSACLOZ to patients with a history of seizures or other predisposing risk factors for seizure (CNS pathology, medications that lower the seizure threshold, alcohol abuse). Caution patients about engaging in any activity where sudden loss of consciousness could cause serious risk to themselves or others [see Dosage and Administration (2.2) and Warnings and Precautions (5.4)].

Myocarditis, Pericarditis, Cardiomyopathy and Mitral Valve Incompetence

Fatal myocarditis and cardiomyopathy have occurred with clozapine treatment. Discontinue VERSACLOZ and obtain a cardiac evaluation upon suspicion of these reactions. Generally, patients with VERSACLOZ-related myocarditis or cardiomyopathy should not be rechallenged with VERSACLOZ. Consider the possibility of myocarditis, pericarditis, or cardiomyopathy if chest pain, tachycardia, palpitations, dyspnea, fever, flu-like symptoms, hypotension, or ECG changes occur. [ see Warnings and Precautions (5.5)].

Increased Mortality in Elderly Patients with Dementia-Related Psychosis

Elderly patients with dementia-related psychosis treated with antipsychotic drugs are at an increased risk of death. VERSACLOZ is not approved for use in patients with dementia- related psychosis [see Warnings and Precautions (5.6)].

1 INDICATIONS AND USAGE

1.1 Treatment-Resistant Schizophrenia

VERSACLOZ is indicated for the treatment of severely ill patients with schizophrenia who fail to respond adequately to standard antipsychotic treatment. Because of the risks of severe neutropenia and of seizure associated with its use, VERSACLOZ should be used only in patients who have failed to respond adequately to standard antipsychotic treatment [see Warnings and Precautions (5.1, 5.4)].

The effectiveness of clozapine in treatment-resistant schizophrenia was demonstrated in a 6-week, randomized, double-blind, active-controlled study comparing clozapine and chlorpromazine in patients who had failed other antipsychotics [see Clinical Studies (14.1)] .

1.2 Reduction in the Risk of Recurrent Suicidal Behavior in Schizophrenia or Schizoaffective Disorders

VERSACLOZ is indicated for reducing the risk of recurrent suicidal behavior in patients with schizophrenia or schizoaffective disorder who are judged to be at chronic risk for re-experiencing suicidal behavior, based on history and recent clinical state. Suicidal behavior refers to actions by a patient that put him/herself at risk for death.

The effectiveness of clozapine in reducing the risk of recurrent suicidal behavior was demonstrated over a two-year treatment period in the InterSePT™ trial [see Clinical Studies (14.2)] .

2 DOSAGE AND ADMINISTRATION

2.1 Absolute Neutrophil Count Testing Prior to VERSACLOZ Initiation

Prior to initiating VERSACLOZ treatment, obtain a baseline absolute neutrophil count (ANC). VERSACLOZ initiation is not recommended in patients with an ANC less than 1500/µL [see Warnings and Precautions (5.1)].

For patients with documented Benign Ethnic Neutropenia (BEN) (also known as Duffy-null associated neutrophil count)), obtain at least two baseline ANC levels. VERSACLOZ initiation is not recommended in patients with BEN with an ANC less than 1000/µL [see Warnings and Precautions (5.1)].

For dosage modifications based on ANC results, see Dosage and Administration (2.4, 2.5).

2.2 Recommended Dosage

To reduce the risk of orthostatic hypotension, bradycardia, and syncope, the recommended starting dosage is much lower than the target dosage [see Warnings and Precautions (5.2)].

The recommended starting oral dosage of VERSACLOZ is 12.5 mg once or twice daily. If well-tolerated, increase the total daily dose in increments of 25 mg to 50 mg per day to achieve a target dosage of 150 mg to 225 mg twice per day by the end of two weeks. Subsequently, may increase the dosage in increments of up to 100 mg once weekly or twice weekly. The maximum recommended VERSACLOZ oral dosage is 450 mg twice daily.

2.3 Important Administration Instructions

Educate patients and caregivers on how to administer VERSACLOZ (see the Instructions for Use). VERSACLOZ can be taken with or without food [ see Clinical Pharmacology (12.3)].

The following are important administration instructions:

- Administer VERSACLOZ orally using the provided oral syringes (1 mL or 9 mL).
- After shaking the VERSACLOZ bottle for 10 seconds, press the syringe adaptor on top of the bottle.
- Insert the oral syringe (1 mL or 9 mL) filled with air into the adapter, dispel the air into the bottle, and then turn the bottle upside down.
- Draw the prescribed amount of the oral suspension from the bottle and immediately dispense directly to the mouth after preparation. Do not store a dose in the syringe for later use.

After use, may wash the oral syringe with warm water and then dry the oral syringe for the next use. The bottle may be closed with the same cap without removing the bottle adapter.

2.4 Dosage Modification Based on ANC Results

Table 1 provides recommended VERSACLOZ dosage modifications based on ANC results [see Warnings and Precautions (5.1)]. For dosage modifications based on ANC results for patients with Benign Ethnic Neutropenia (BEN) (also known as Duffy-null associated neutrophil count), see Table 2 [see Dosage and Administration (2.5)].

Table 1: VERSACLOZ Dosage Modifications Based on ANC Results and Frequency of ANC Testing

Recommended Dosage Modification | Recommended Frequency of ANC Teting During VERSACLOZ Treatment
ANC Within Normal Range (≥1500/µL)
No dosage modification: continue treatment | - Day 1 to Month 6: Weekly - Month 7 to Month 12: Every 2 weeks - Month 13 and thereafter: Every month
No dosage modification: continue treatment | If VERSACLOZ treatment is reinitiated after a dosage interruption (e.g., patient had neutropenia which required dosage interruption and now has a normal ANC level) for:; - < 30 days, continue the previous ANC testing frequency - ≥ 30 days, obtain ANC tests according to the frequency for patients who initiate treatment
Mild Neutropenia (ANC between 1000 to 1499/µL)^1
No dosage modification: continue treatment | - Three times weekly - Once ANC ≥ 1500/µL, recommend returning to the patient’s last Normal RangeANC testing frequency
Moderate Neutropenia (ANC between 500 to 999/µL)^1
- Interrupt treatment and recommend hematology consultation - Resume treatment once ANC ≥1000/µL - Daily - Once ANC ≥ 1000/µL, three times weekly - Once ANC ≥ 1500/µL, test weekly for 4 weeks. If ANC ≥ 1500/µL after monitoring weekly for 4 weeks, return to the patient’s last Normal RangeANC testing frequency
Severe Neutropenia (ANC less than 500/µL)^1
Discontinue treatment and recommend hematology consultation | - Daily - Once ANC ≥ 1000/µL, three times weekly - Once ANC ≥ 1500/µL, if the benefits outweigh the risks of restarting treatment, resume treatment and obtain ANC tests according to the frequency for patients who initiate treatment

^1Confirm all initial reports of ANC less than 1500/μL with a repeat ANC measurement within 24 hours

2.5 Dosage Modifications Based on ANC Results for Patients with Benign Ethnic Neutropenia

Table 2 provides recommended VERSACLOZ dosage modifications based on ANC results for patients with Benign Ethnic Neutropenia (BEN) (also known as Duffy-null associated neutrophil count). [see Warnings and Precautions (5.1)]. For dosage modifications based on ANC results for patients without BEN, see Table 1 [see Dosage and Administration (2.4)].

Table 2: Dosage Modifications Based on ANC Results and Frequency of ANC Testing in Patients with Benign Ethnic Neutropenia^1

Recommended Dosage Modification | Recommended Frequency of ANC Teting During VERSACLOZ Treatment in Patients with BEN^1
ANC Within the Normal Range for Patients with BEN (≥ 1000/µL)
No dosage modification: continue treatment | - Day 1 to Month 6: Weekly - Month 7 to Month 12: Every 2 weeks - Month 13 and thereafter: Monthly
No dosage modification: continue treatment | If VERSACLOZ treatment is reinitiated after a dosage interruption (e.g., patient had neutropenia which required dosage interruption and now their ANC (≥ 1000/µL and ≥ the patient’s ANC baseline prior to treatment) for:; - < 30 days, continue the previous ANC testing frequency - ≥ 30 days, obtain ANC tests according to the frequency for patients with BEN who initiate treatment
Neutropenia in Patients with BEN (ANC level between 500 to 999/μL)^2
- Recommend hematology consultation - No dosage modification: continue treatment - Three times weekly - Once ANC ≥ 1000/μL and ≥ the patient’s ANC baseline, obtain ANC tests weekly for 4 weeks - If ANC ≥1000/μL and ≥ the patient’s baseline after monitoring for 4 weeks, return to the patient’s last Normal ANC Rangetesting frequency for patients with BEN.
Severe Neutropenia in Patients with BEN (ANC level less than 500/μL)^2
Discontinue treatment and recommend hematology consultation | - Daily - Once ANC ≥ 500/µL, obtain ANC three times weekly - Once ANC ≥ 1000/µL and ≥ the patient’s baseline, if the benefits outweigh the risks of restarting treatment, resume treatment and obtain ANC tests according to the frequency for patients with BEN who initiate treatment

^1Benign Ethnic Neutropenia (BEN) is also known as Duffy-null associated neutrophil count.

^2Confirm all initial reports of ANC less than 1500/μL with a repeat ANC measurement within 24 hours

2.6 Discontinuation of VERSACLOZ Treatment

If discontinuing VERSACLOZ in patients with:

- Moderate or severe neutropenia, see Table 1 [see Dosage and Administration (2.4)].
- Normal or mild neutropenia, reduce the dosage gradually over a period of 1 to 2 weeks, and continue monitoring ANC levels until their ANC is ≥1500/μL.

If discontinuing VERSACLOZ in patients with Benign Ethnic Neutropenia (BEN) (also known as Duffy-null associated neutrophil count) with:

- Neutropenia, see Table 2 [see Dosage and Administration (2.5)].
- ANC within their normal range of ANC reduce the dosage gradually over a period of 1 to 2 weeks.

When discontinuing VERSACLOZ, monitor patients for the symptoms related to psychotic recurrence and cholinergic rebound (e.g., profuse sweating, headache, nausea, vomiting, diarrhea).

2.7 Restarting VERSACLOZ Treatment After Interrupting VERSACLOZ

When restarting VERSACLOZ in patients who have interrupted VERSACLOZ treatment, use a lower dosage to minimize the risk of hypotension, bradycardia, and syncope [see Warnings and Precautions (5.2)].

- If one day’s dosage is missed, resume VERSACLOZ treatment at 40% to 50% of the previous dosage.
- If two days of dosing is missed, resume VERSACLOZ treatment at approximately 25% of the previous dosage.
- For longer interruptions, restart VERSACLOZ treatment with a dosage of 12.5 mg once or twice daily. If this dosage is well-tolerated, may increase the dosage to the previous dosage more quickly than recommended than for initial VERSACLOZ treatment.

2.8 Dosage Modifications for Drug Interactions

See Table 3 for recommended dosage modifications to reduce the risk of VERSACLOZ associated adverse reactions or reduce the risk of lower effectiveness [see Drug Interactions (7)].

Table 3: VERSACLOZ Dosage Modifications for Drug Interactions

Strong CYP1A2 Inhibitors | Administer one third of the VERSACLOZ dosage.
Moderate or Weak CYP1A2 Inhibitors | Consider reducing the VERSACLOZ dosage if necessary.
CYP2D6 or CYP3A4 Inhibitors | Consider reducing the VERSACLOZ dosage if necessary.
Strong CYP3A4 Inducers | Concomitant use is not recommended. However, if concomitant use is necessary, it may be necessary to increase the VERSACLOZ dosage. Monitor for decreased effectiveness.
Moderate or weak CYP1A2 or CYP3A4 Inducers | Consider increasing the VERSACLOZ dosage if necessary.

2.9 Dosage Recommendations in Patients with Renal or Hepatic Impairment, or CYP2D6 Poor Metabolizers

It may be necessary to reduce the VERSACLOZ dosage in patients with significant renal impairment or hepatic impairment, or in CYP2D6 poor metabolizers [see Use in Specific Populations (8.6, 8.7)].

3 DOSAGE FORMS AND STRENGTHS

VERSACLOZ is available as a free-flowing yellow oral suspension. Each mL contains 50 mg of clozapine.

4 CONTRAINDICATIONS

VERSACLOZ is contraindicated in patients with a history of hypersensitivity to clozapine (e.g., photosensitivity, vasculitis, erythema multiforme, or Stevens-Johnson Syndrome) or any other component of VERSACLOZ [see Adverse Reactions (6.2)] .

5 WARNINGS AND PRECAUTIONS

5.1 Severe Neutropenia

VERSACLOZ has caused severe neutropenia (absolute neutrophil count (ANC) less than 500/μL) [see Adverse Reactions (6.1, 6.2)]and is associated with an increased risk of serious and potentially fatal infections. Severe neutropenia occurred in a small percentage of VERSACLOZ-treated patients. The risk of severe neutropenia appears greatest during the first 18 weeks of VERSACLOZ treatment. The mechanism by which VERSACLOZ causes neutropenia is unknown. Neutropenia is not dose dependent.

Consider a hematology consultation before initiating VERSACLOZ treatment or during

treatment.

ANC Monitoring and Dosage Modifications

Prior to initiating VERSACLOZ treatment, obtain a baseline ANC. VERSACLOZ initiation is not recommended in patients with a baseline ANC less than 1500/μL. Throughout VERSACLOZ treatment, regularly monitor ANC. Table 1 provides recommendations for dosage modifications (dosage interruption and treatment discontinuation), based on ANC levels, during VERSACLOZ treatment and frequency of ANC monitoring [see Dosage and Administration (2.4)].

ANC Monitoring and Dosage Modification in Patients with Benign Ethnic Neutropenia

Patients with with Benign Ethnic Neutropenia (BEN) (also known as Duffy-null associated neutrophil count) generally have lower baseline neutrophil counts but they are not at higher risk for developing infections, and they are not at increased risk for developing VERSACLOZ-induced neutropenia.

For patients with documented BEN, obtain at least two baseline ANC levels prior to VERSACLOZ initiation. VERSACLOZ initiation is not recommended in patients with BEN with an ANC less than 1000/μL. There are different ANC dosage modification recommendations in VERSACLOZ-treated patients with BEN due to their lower baseline ANC levels. Table 2 provides recommendations on dosage modifications (dosage interruption and treatment discontinuation), based on ANC monitoring, during VERSACLOZ treatment in patients with BEN and recommended frequency of ANC testing [see Dosage and Administration (2.5)].

Management of VERSACLOZ-Treated Patients Who Develop a Fever

For patients who develop a fever during VERSACLOZ treatment:

- Interrupt VERSACLOZ in those who develop a temperature of 101.3 °F (38.5 °C) or greater and obtain an ANC level.
- If the ANC is less than 1000/μL in patients without BEN, initiate appropriate workup and treatment for infection. Refer to Table 1 for dosage modifications based on ANC monitoring [see Dosage and Administration (2.4)].

In patients with fever and a normal neutrophil count, see Warnings and Precautions (5.11)for neuroleptic malignant syndrome and Warnings and Precautions (5.13)for fever.

Restarting VERSACLOZ in Patients Who Recovered from Severe Neutropenia

Generally, do not rechallenge patients with VERSACLOZ in those who experienced severe neutropenia. However, for some patients who had resolution of their VERSACLOZ-related severe neutropenia after stopping VERSACLOZ, the risk of schizophrenia exacerbation from not restarting VERSACLOZ treatment may be greater than the risk of neutropenia reoccurrence from restarting VERSACLOZ (e.g., patients who have no treatment options other than VERSACLOZ).

Concomitant Use of VERSACLOZ with Other Drugs Known to Cause Neutropenia

If VERSACLOZ is used concomitantly with another drug known to cause neutropenia, consider more frequently ANC monitoring than the recommendations provided in Table 1 and Table 2.

5.2 Orthostatic Hypotension, Bradycardia, and Syncope

Hypotension, bradycardia, syncope, and cardiac arrest have occurred with clozapine treatment. The risk is highest during the initial titration period, particularly with rapid dose-escalation. These reactions can occur with the first dose, at doses as low as 12.5 mg. These reactions can be fatal. The syndrome is consistent with neurally mediated reflex bradycardia (NMRB).

Treatment must begin at a maximum dose of 12.5 mg once daily or twice daily. The total daily dose can be increased in increments of 25 mg to 50 mg per day, if well-tolerated, to a target dose of 300 mg to 450 mg per day (administered in divided doses) by the end of 2 weeks. Subsequently, the dose can be increased weekly or twice weekly, in increments of up to 100 mg. The maximum dose is 900 mg per day. Use cautious titration and a divided dosage schedule to minimize the risk of serious cardiovascular reactions [see Dosage and Administration (2.2)] . Consider reducing the dose if hypotension occurs. When restarting VERSACLOZ in patients who have had even a brief interruption in treatment with VERSACLOZ, the dosage must be reduced. This is necessary to minimize the risk of hypotension, bradycardia, and syncope [see Dosage and Administration (2.6)].

Use VERSACLOZ cautiously in patients with cardiovascular disease (history of myocardial infarction or ischemia, heart failure, or conduction abnormalities), cerebrovascular disease, and conditions which would predispose patients to hypotension (e.g., concomitant use of antihypertensives, dehydration and hypovolemia).

5.3 Falls

VERSACLOZ may cause somnolence, postural hypotension, and motor and sensory instability, which may lead to falls and, consequently, fractures or other injuries. For patients with diseases, conditions, or medications that could exacerbate these effects, complete fall risk assessments when initiating antipsychotic treatment and recurrently for patients on long-term antipsychotic treatment.

5.4 Seizures

Seizure has been estimated to occur in association with clozapine use at a cumulative incidence at one year of approximately 5%, based on the occurrence of one or more seizures in 61 of 1743 patients exposed to clozapine during its clinical testing prior to domestic marketing (i.e., a crude rate of 3.5%). The risk of seizure is dose-related. Initiate treatment with a low dose (12.5 mg), titrate slowly, and use divided dosing.

Use caution when administering VERSACLOZ to patients with a history of seizures or other predisposing risk factors for seizure (e.g., head trauma or other CNS pathology, use of medications that lower the seizure threshold, or alcohol abuse). Because of the substantial risk of seizure associated with VERSACLOZ use, caution patients about engaging in any activity where sudden loss of consciousness could cause serious risk to themselves or others (e.g., driving an automobile, operating complex machinery, swimming, climbing).

5.5 Myocarditis, Pericarditis, Cardiomyopathy and Mitral Valve Incompetence

Myocarditis, pericarditis, and cardiomyopathy have occurred with the use of clozapine. These reactions can be fatal. Discontinue VERSACLOZ and obtain a cardiac evaluation upon suspicion of myocarditis, pericarditis, or cardiomyopathy. Generally, patients with a history of clozapine-associated myocarditis, pericarditis, or cardiomyopathy should not be rechallenged with VERSACLOZ. However, if the benefit of VERSACLOZ treatment is judged to outweigh the potential risks of recurrence, the clinician may consider rechallenge with VERSACLOZ in consultation with a cardiologist.

Myocarditis and pericarditis most frequently present within the first two months of clozapine treatment. Symptoms of cardiomyopathy generally occur later than clozapine-associated myocarditis or pericarditis and usually after 8 weeks of treatment. However, myocarditis, pericarditis, and cardiomyopathy can occur at any period during treatment with VERSACLOZ. In patients who are diagnosed with cardiomyopathy while taking clozapine mitral valve incompetence has been reported.

5.6 Increased Mortality in Elderly Patients with Dementia-Related Psychosis

Elderly patients with dementia-related psychosis treated with antipsychotic drugs are at an increased risk of death. Analyses of 17 placebo-controlled trials (modal duration of 10 weeks), largely in patients taking atypical antipsychotic drugs, revealed a risk of death in drug-treated patients of between 1.6 to 1.7 times the risk of death in placebo-treated patients. Over the course of a typical 10-week controlled trial, the rate of death in drug-treated patients was about 4.5%, compared to a rate of about 2.6% in the placebo group. Although the causes of death were varied, most of the deaths appeared to be either cardiovascular (e.g., heart failure, sudden death) or infectious (e.g., pneumonia) in nature. Observational studies suggest that, similar to atypical antipsychotic drugs, treatment with conventional antipsychotic drugs may increase mortality in this population. The extent to which the findings of increased mortality in observational studies may be attributed to the antipsychotic drug as opposed to some characteristic(s) of the patients is not clear. VERSACLOZ is not approved for the treatment of patients with dementia-related psychosis [see Boxed Warning].

5.7 Gastrointestinal Hypomotility and Severe Complications

Severe gastrointestinal adverse reactions have occurred with the use of VERSACLOZ, primarily due to its potent anticholinergic effects and resulting gastrointestinal hypomotility. In post marketing experience, reported effects range from constipation to paralytic ileus. Increased frequency of constipation and delayed diagnosis and treatment increased the risk of severe complications of gastrointestinal hypomotility, which can result in fecal impaction, megacolon, and intestinal obstruction, ischemia, infarction, perforation, ulceration, or necrosis [see Adverse Reaction (6.2)]. These reactions have resulted in hospitalization, surgery, and death. The risk for severe adverse reactions is further increased with anticholinergic medications (and other medications that decrease gastrointestinal peristalsis); therefore, concomitant use should be avoided when possible [see Warnings and Precautions (5.15), Drug Interactions (7.1)].

Prior to initiating VERSACLOZ, screen for constipation and treat as necessary. Subjective symptoms of constipation may not accurately reflect the degree of gastrointestinal hypomotility in VERSACLOZ treated patients. Therefore, reassess bowel function frequently with careful attention to any changes in the frequency or character of bowel movements, as well as signs and symptoms of complications of hypomotility (e.g., nausea, vomiting, abdominal distension, abdominal pain). If constipation or gastrointestinal hypomotility are identified, monitor closely and treat promptly with appropriate laxatives, as necessary, to prevent severe complications. Consider prophylactic laxatives in high risk patients.

5.8 Eosinophilia

Eosinophilia, defined as a blood eosinophil count of greater than 700/μL, has occurred with clozapine treatment. In clinical trials, approximately 1% of patients developed eosinophilia. Clozapine-related eosinophilia usually occurs during the first month of treatment. In some patients, it has been associated with myocarditis, pancreatitis, hepatitis, colitis, and nephritis. Such organ involvement could be consistent with a drug reaction with eosinophilia and systemic symptoms syndrome (DRESS), also known as drug induced hypersensitivity syndrome (DIHS). If eosinophilia develops during VERSACLOZ treatment, evaluate promptly for signs and symptoms of systemic reactions, such as rash or other allergic symptoms, myocarditis, or other organ-specific disease associated with eosinophilia. If clozapine-related systemic disease is suspected, discontinue VERSACLOZ immediately.

If a cause of eosinophilia unrelated to clozapine is identified (e.g., asthma, allergies, collagen vascular disease, parasitic infections, and specific neoplasms), treat the underlying cause and continue VERSACLOZ.

Clozapine-related eosinophilia has also occurred in the absence of organ involvement and can resolve without intervention. There are reports of successful rechallenge after discontinuation of clozapine, without recurrence of eosinophilia. In the absence of organ involvement, continue VERSACLOZ under careful monitoring. If the total eosinophil count continues to increase over several weeks in the absence of systemic disease, the decision to interrupt VERSACLOZ therapy and rechallenge after the eosinophil count decreases should be based on the overall clinical assessment, in consultation with an internist or hematologist.

5.9 QT Interval Prolongation

QT prolongation, Torsades de Pointes and other life-threatening ventricular arrhythmias, cardiac arrest, and sudden death have occurred with clozapine treatment. When prescribing VERSACLOZ, consider the presence of additional risk factors for QT prolongation and serious cardiovascular reactions. Conditions that increase these risks include the following: history of QT prolongation, long QT syndrome, family history of long QT syndrome or sudden cardiac death, significant cardiac arrhythmia, recent myocardial infarction, uncompensated heart failure, treatment with other medications that cause QT prolongation, treatment with medications that inhibit the metabolism of VERSACLOZ, and electrolyte abnormalities.

Prior to initiating treatment with VERSACLOZ, perform a careful physical examination, medical history, and concomitant medication history. Consider obtaining a baseline ECG and serum chemistry panel. Correct electrolyte abnormalities. Discontinue VERSACLOZ if the QTc interval exceeds 500 msec. If patients experience symptoms consistent with Torsades de Pointes or other arrhythmias, (e.g., syncope, presyncope, dizziness, or palpitations), obtain a cardiac evaluation and discontinue VERSACLOZ.

Use caution when administering concomitant medications that prolong the QT interval or inhibit the metabolism of VERSACLOZ. Drugs that cause QT prolongation include: specific antipsychotics (e.g., ziprasidone, iloperidone, chlorpromazine, thioridazine, mesoridazine, droperidol, pimozide), specific antibiotics (e.g., erythromycin, gatifloxacin, moxifloxacin, sparfloxacin), Class 1A antiarrhythmic medications (e.g., quinidine, procainamide) or Class III antiarrhythmic (e.g., amiodarone, sotalol), and others (e.g., pentamidine, levomethadyl acetate, methadone, halofantrine, mefloquine, dolasetron mesylate, probucol or tacrolimus). VERSACLOZ is primarily metabolized by CYP isoenzymes 1A2, 2D6, and 3A4. Concomitant treatment with inhibitors of these enzymes can increase the concentration of VERSACLOZ [see Drug Interactions (7.1)and Clinical Pharmacology (12.3)].

Hypokalemia and hypomagnesemia increase the risk of QT prolongation. Hypokalemia can result from diuretic therapy, diarrhea, and other causes. Use caution when treating patients at risk for significant electrolyte disturbance, particularly hypokalemia. Obtain baseline measurements of serum potassium and magnesium levels, and periodically monitor electrolytes. Correct electrolyte abnormalities before initiating treatment with VERSACLOZ.

5.10 Metabolic Changes

Atypical antipsychotic drugs, including VERSACLOZ, have been associated with metabolic changes that can increase cardiovascular and cerebrovascular risk. These metabolic changes include hyperglycemia, dyslipidemia, and body weight gain. While atypical antipsychotic drugs may produce some metabolic changes, each drug in the class has its own specific risk profile.

Hyperglycemia and Diabetes Mellitus

Hyperglycemia, in some cases extreme and associated with ketoacidosis or hyperosmolar coma or death, has been reported in patients treated with atypical antipsychotics including VERSACLOZ. Assessment of the relationship between atypical antipsychotic use and glucose abnormalities is complicated by the possibility of an increased background risk of diabetes mellitus in patients with schizophrenia and the increasing incidence of diabetes mellitus in the general population. Given these confounders, the relationship between atypical antipsychotic use and hyperglycemia-related adverse reactions is not completely understood. However, epidemiological studies suggest an increased risk of treatment-emergent, hyperglycemia-related adverse reactions in patients treated with the atypical antipsychotics. Precise risk estimates for hyperglycemia-related adverse reactions in patients treated with atypical antipsychotics are not available.

Patients with an established diagnosis of diabetes mellitus who are started on VERSACLOZ should be monitored regularly for worsening of glucose control. Patients with risk factors for diabetes mellitus (e.g., obesity, family history of diabetes) who are starting treatment with atypical antipsychotics should undergo fasting blood glucose testing at the beginning of treatment and periodically during treatment. Any patient treated with atypical antipsychotics should be monitored for symptoms of hyperglycemia including polydipsia, polyuria, polyphagia, and weakness. Patients who develop symptoms of hyperglycemia during treatment with atypical antipsychotics should undergo fasting blood glucose testing. In some cases, hyperglycemia has resolved when the atypical antipsychotic was discontinued; however, some patients required continuation of anti-diabetic treatment despite discontinuation of the suspect drug.

In a pooled data analysis of 8 studies in adult subjects with schizophrenia, the mean changes in fasting glucose concentration in the clozapine and chlorpromazine groups were +11 mg/dL and +4 mg/dL respectively. A higher proportion of the clozapine group demonstrated categorical increases from baseline in fasting glucose concentrations, compared to the chlorpromazine group (Table 4). The clozapine doses were 100-900 mg per day (mean modal dose: 512 mg per day). The maximum chlorpromazine dose was 1800 mg per day (mean modal dose: 1029 mg per day). The median duration of exposure was 42 days for clozapine and chlorpromazine.

Table 4: Categorical Changes in Fasting Glucose Level in Studies in Adult Subjects with Schizophrenia

Laboratory Parameter | Category Change (at least once) from baseline | Treatment Arm | N | n (%)
Fasting Glucose | Normal (<100 mg/dL) to High (≥126 mg/dL) | Clozapine | 198 | 53 (27)
Fasting Glucose | Normal (<100 mg/dL) to High (≥126 mg/dL) | Chlorpromazine | 135 | 14 (10)
Fasting Glucose | Borderline (100 to 125 mg/dL) to High (≥126 mg/dL) | Clozapine | 57 | 24 (42)
Fasting Glucose | Borderline (100 to 125 mg/dL) to High (≥126 mg/dL) | Chlorpromazine | 43 | 12 (28)

Dyslipidemia

Undesirable alterations in lipids have occurred in patients treated with atypical antipsychotics, including VERSACLOZ. Clinical monitoring, including baseline and periodic follow-up lipid evaluations in patients using VERSACLOZ, is recommended.

In a pooled data analysis of 10 studies in adult subjects with schizophrenia, clozapine treatment was associated with increases in serum total cholesterol. No data were collected on LDL and HDL cholesterol. The mean increase in total cholesterol was 13 mg/dL in the clozapine group and 15 mg/dL in the chlorpromazine group. In a pooled data analysis of 2 studies in adult subjects with schizophrenia, clozapine treatment was associated with increases in fasting serum triglyceride. The mean increase in fasting triglyceride was 71 mg/dL (54%) in the clozapine group and 39 mg/dL (35%) in the chlorpromazine group (Table 5). In addition, clozapine treatment was associated with categorical increases in serum total cholesterol and triglyceride, as illustrated in Table 6. The proportion of patients with categorical increases in total cholesterol or fasting triglyceride increased with the duration of exposure. The median duration of clozapine and chlorpromazine exposure was 45 days and 38 days, respectively. The clozapine dose range was 100 mg to 900 mg daily; the maximum chlorpromazine dose was 1800 mg daily.

Table 5: Mean Changes in Total Cholesterol and Triglyceride Concentration in Studies in Adult Subjects with Schizophrenia

Treatment Arm | Baseline total cholesterol concentration (mg/dL) | Change from baseline mg/dL (%)
Clozapine (N=334) | 184 | +13 (7)
Chlorpromazine (N=185) | 182 | +15 (8)
 | Baseline triglyceride concentration (mg/dL) | Change from baseline mg/dL (%)
Clozapine (N=6) | 130 | +71 (54)
Chlorpromazine (N=7) | 110 | +39 (35)

Table 6: Categorical Changes in Lipid Concentrations in Studies in Adult Subjects with Schizophrenia

Laboratory Parameter | Category Change (at least once) from Baseline | Treatment Arm | N | n (%)
Total Cholesterol (random or fasting) | Increase by ≥ 40 mg/dL | Clozapine | 334 | 111 (33)
Total Cholesterol (random or fasting) | Increase by ≥ 40 mg/dL | Chlorpromazine | 185 | 46 (25)
Total Cholesterol (random or fasting) | Normal (<200 mg/dL) to High (≥240 mg/dL) | Clozapine | 222 | 18 (8)
Total Cholesterol (random or fasting) | Normal (<200 mg/dL) to High (≥240 mg/dL) | Chlorpromazine | 132 | 3 (2)
Total Cholesterol (random or fasting) | Borderline (200 - 239 mg/dL) to High (≥240 mg/dL) | Clozapine | 79 | 30 (38)
Total Cholesterol (random or fasting) | Borderline (200 - 239 mg/dL) to High (≥240 mg/dL) | Chlorpromazine | 34 | 14 (41)
Triglycerides (fasting) | Increase by ≥50 mg/dL | Clozapine | 6 | 3 (50)
Triglycerides (fasting) | Increase by ≥50 mg/dL | Chlorpromazine | 7 | 3 (43)
Triglycerides (fasting) | Normal (<150 mg/dL) to High (≥200 mg/dL) | Clozapine | 4 | 0 (0)
Triglycerides (fasting) | Normal (<150 mg/dL) to High (≥200 mg/dL) | Chlorpromazine | 6 | 2 (33)
Triglycerides (fasting) | Borderline (≥150 mg/dL and <200 mg/dL) to High (≥200 mg/dL) | Clozapine | 1 | 1 (100)
Triglycerides (fasting) | Borderline (≥150 mg/dL and <200 mg/dL) to High (≥200 mg/dL) | Chlorpromazine | 1 | 0 (0)

Weight Gain

Weight gain has occurred with the use of antipsychotics, including VERSACLOZ. Monitor weight during treatment with VERSACLOZ. Table 7 summarizes the data on weight gain by the duration of exposure pooled from 11 studies with clozapine and active comparators. The median duration of exposure was 609, 728, and 42 days, in the clozapine, olanzapine, and chlorpromazine group, respectively.

Table 7: Mean Change in Body Weight (kg) by duration of exposure from studies in adult subjects with schizophrenia

Metabolic parameter | Exposure duration | Clozapine (N=669) |  | Olanzapine (N=442) |  | Chlorpromazine (N=155)
Metabolic parameter | Exposure duration | n | Mean | n | Mean | n | Mean
Weight change from baseline | 2 weeks (Day 11 – 17) | 6 | +0.9 | 3 | +0.7 | 2 | -0.5
Weight change from baseline | 4 weeks (Day 21 – 35) | 23 | +0.7 | 8 | +0.8 | 17 | +0.6
Weight change from baseline | 8 weeks (Day 49 – 63) | 12 | +1.9 | 13 | +1.8 | 16 | +0.9
Weight change from baseline | 12 weeks (Day 70 – 98) | 17 | +2.8 | 5 | +3.1 | 0 | 0
Weight change from baseline | 24 weeks (154 – 182) | 42 | -0.6 | 12 | +5.7 | 0 | 0
Weight change from baseline | 48 weeks (Day 322 – 350) | 3 | +3.7 | 3 | +13.7 | 0 | 0

Table 8 summarizes pooled data from 11 studies in adult subjects with schizophrenia demonstrating weight gain ≥7% of body weight relative to baseline. The median duration of exposure was 609, 728, and 42 days, in the clozapine, olanzapine, and chlorpromazine group, respectively.

Table 8: Proportion of adult subjects in schizophrenia studies with weight gain ≥7% relative to baseline body weight

Weight change | Clozapine | Olanzapine | Chlorpromazine
N | 669 | 442 | 155
≥7% (inclusive) | 236 (35%) | 203 (46%) | 13 (8%)

5.11 Neuroleptic Malignant Syndrome

Antipsychotic drugs including VERSACLOZ can cause a potentially fatal symptom complex referred to as Neuroleptic Malignant Syndrome (NMS). Clinical manifestations of NMS include hyperpyrexia, muscle rigidity, altered mental status, and autonomic instability (irregular pulse or blood pressure, tachycardia, diaphoresis, and cardiac dysrhythmias). Associated findings can include elevated creatine phosphokinase (CPK), myoglobinuria, rhabdomyolysis, and acute renal failure.

The diagnostic evaluation of patients with this syndrome is complicated. It is important to consider the presence of other serious medical conditions (e.g., severe neutropenia, infection, heat stroke, primary CNS pathology, central anticholinergic toxicity, extrapyramidal symptoms, and drug fever).

The management of NMS should include (1) immediate discontinuation of antipsychotic drugs and other drugs not essential to concurrent therapy, (2) intensive symptomatic treatment and medical monitoring, and (3) treatment of co-morbid medical conditions. There is no general agreement about specific pharmacological treatments for NMS.

If a patient requires antipsychotic drug treatment after recovery from NMS, the potential reintroduction of drug therapy should be carefully considered. NMS can recur. Monitor closely if restarting treatment with antipsychotics.

NMS has occurred with clozapine monotherapy and with concomitant CNS-active medications, including lithium.

5.12 Hepatotoxicity

Severe, life threatening, and in some cases fatal hepatotoxicity including hepatic failure, hepatic necrosis, and hepatitis have been reported in patients treated with clozapine [see Adverse Reactions (6.2)]. Monitor for the appearance of signs and symptoms of hepatotoxicity such as fatigue, malaise, anorexia, nausea, jaundice, bilirubinemia, coagulopathy, and hepatic encephalopathy. Perform serum tests for liver injury and consider permanently discontinuing treatment if hepatitis or transaminase elevations combined with other systemic symptoms are due to clozapine.

5.13 Fever

During clozapine therapy, patients have experienced transient, clozapine-related fever. The peak incidence is within the first 3 weeks of treatment. While this fever is generally benign and self-limited, it may necessitate discontinuing treatment. The fever can be associated with an increase or decrease in WBC count. Carefully evaluate patients with fever to rule out severe neutropenia or infection[see Warnings and Precautions (5.1)]. Consider the possibility of NMS [see Warnings and Precautions (5.11)].

5.14 Pulmonary Embolism

Pulmonary embolism and deep vein thrombosis have occurred in patients treated with clozapine. Consider the possibility of pulmonary embolism in patients who present with deep vein thrombosis, acute dyspnea, chest pain, or with other respiratory signs and symptoms. Whether pulmonary embolus and deep vein thrombosis can be attributed to clozapine or some characteristic(s) of patients is not clear.

5.15 Anticholinergic Toxicity

VERSACLOZ has potent anticholinergic effects. Treatment with VERSACLOZ can result in CNS and peripheral anticholinergic toxicity, especially at higher dosages or in overdose situations [see Overdosage (10)].Use with caution in patients with a current diagnosis or prior history of constipation, urinary retention, clinically significant prostatic hypertrophy, or other conditions in which anticholinergic effects can lead to significant adverse reactions. When possible, avoid concomitant use with other anticholinergic medications because the risk for anticholinergic toxicity or severe gastrointestinal adverse reactions is increased [see Warnings and Precautions (5.7), Drug Interactions (7.1)].

5.16 Interference with Cognitive and Motor Performance

VERSACLOZ can cause sedation and impairment of cognitive and motor performance. Caution patients about operating hazardous machinery, including automobiles, until they are reasonably certain that VERSACLOZ does not affect them adversely. These reactions may be dose-related. Consider reducing the dose if they occur.

5.17 Tardive Dyskinesia

Tardive dyskinesia (TD) has occurred in patients treated with antipsychotic drugs, including VERSACLOZ. The syndrome consists of potentially irreversible, involuntary, dyskinetic movements. The risk of TD and the likelihood that it will become irreversible are believed to increase with greater durations of treatment and higher total cumulative doses. However, the syndrome can develop after relatively brief treatment periods at low doses. Prescribe VERSACLOZ in a manner that is most likely to minimize the risk of developing TD. Use the lowest effective dose and the shortest duration necessary to control symptoms. Periodically assess the need for continued treatment. Consider discontinuing treatment if TD occurs. However, some patients may require treatment with VERSACLOZ despite the presence of the syndrome.

TD may remit partially or completely if treatment is discontinued. Antipsychotic treatment, itself, may suppress (or partially suppress) the signs and symptoms, and it has the potential to mask the underlying process. The effect of symptom suppression on the long-term course of TD is unknown.

5.18 Cerebrovascular Adverse Reactions

In controlled trials, elderly patients with dementia-related psychosis treated with some atypical antipsychotics had an increased risk (compared to placebo) of cerebrovascular adverse reactions (e.g., stroke, transient ischemic attack), including fatalities. The mechanism for this increased risk is not known. An increased risk cannot be excluded for VERSACLOZ or other antipsychotics or other patient populations. VERSACLOZ should be used with caution in patients with risk factors for cerebrovascular adverse reactions.

5.19 Recurrence of Psychosis and Cholinergic Rebound after Abrupt Discontinuation of VERSACLOZ

If abrupt discontinuation of VERSACLOZ is necessary (because of severe neutropenia or another medical condition, for example) [see Dosage and Administration (2.6), Warnings and Precautions (5.1)] , monitor carefully for the recurrence of psychotic symptoms and adverse reactions related to cholinergic rebound, such as profuse sweating, headache, nausea, vomiting and diarrhea.

6 ADVERSE REACTIONS

The following adverse reactions are discussed in more detail in other sections of the labeling:

- Severe Neutropenia [see Warnings and Precautions (5.1)].
- Orthostatic Hypotension, Bradycardia, and Syncope [see Warnings and Precautions (5.2)].
- Falls [see Warnings and Precautions (5.3)]
- Seizures [see Warnings and Precautions (5.4)].
- Myocarditis, Pericarditis, Cardiomyopathy and Mitral Valve Incompetence [see Warnings and Precautions (5.5)].
- Increased Mortality in Elderly Patients with Dementia-Related Psychosis [see Warnings and Precautions (5.6)].
- Gastrointestinal Hypomotility and Severe Complications [see Warnings and Precautions (5.7)].
- Eosinophilia [see Warnings and Precautions (5.8)].
- QT Interval Prolongation [see Warnings and Precautions (5.9)].
- Metabolic Changes (Hyperglycemia and Diabetes Mellitus, Dyslipidemia, and Weight Gain) [see Warnings and Precautions (5.10)].
- Neuroleptic Malignant Syndrome [see Warnings and Precautions (5.11)].
- Hepatotoxicity [see Warnings and Precautions (5.12)].
- Fever [see Warnings and Precautions (5.13)].
- Pulmonary Embolism [see Warnings and Precautions (5.14)].
- Anticholinergic Toxicity [see Warnings and Precautions (5.15)].
- Interference with Cognitive and Motor Performance [see Warnings and Precautions (5.16)].
- Tardive Dyskinesia [see Warnings and Precautions (5.17)].
- Cerebrovascular Adverse Reactions [see Warnings and Precautions (5.18)].
- Recurrence of Psychosis and Cholinergic Rebound after Abrupt Discontinuation [see Warnings and Precautions (5.19)].

6.1 Clinical Trials Experience

Because clinical trials are conducted under widely varying conditions, adverse reaction rates observed in the clinical trials of a drug cannot be directly compared to rates in the clinical trials of another drug and may not reflect the rates observed in clinical practice.The most commonly reported adverse reactions (>5%) across clozapine clinical trials were: CNS reactions, including sedation, dizziness/vertigo, headache, and tremor; cardiovascular reactions, including tachycardia, hypotension, and syncope; autonomic nervous system reactions, including hypersalivation, sweating, dry mouth, and visual disturbances; gastrointestinal reactions, including constipation and nausea; and fever. Table 9 summarizes the most commonly reported adverse reactions (>5%) in clozapine-treated patients (compared to chlorpromazine-treated patients) in the pivotal, 6-week, controlled trial in treatment-resistant schizophrenia.

Table 9: Common Adverse Reactions (≥5%) in the 6-Week, Randomized, Chlorpromazine-controlled Trial in Treatment-Resistant Schizophrenia

Adverse Reaction | Clozapine (N=126) (%) | Chlorpromazine (N=142) (%)
Sedation Tachycardia Constipation Dizziness Hypotension Fever (hyperthermia) Hypersalivation Hypertension Headache Nausea/vomiting Dry mouth | 21 17 16 14 13 13 13 12 10 10 5 | 13 11 12 16 38 4 1 5 10 12 20

Table 10 summarizes the adverse reactions reported in clozapine-treated patients at a frequency of 2% or greater across all clozapine studies (excluding the 2-year InterSePT™Study). These rates are not adjusted for duration of exposure.

Table 10: Adverse Reactions (≥2%) Reported in Clozapine-treated Patients (N=842) across all Clozapine Studies (excluding the 2-year InterSePT™ Study)

Body System Adverse Reaction | Clozapine N=842 Percentage of Patients
Central Nervous System Drowsiness/Sedation Dizziness/Vertigo Headache Tremor; Syncope Disturbed Sleep/Nightmares Restlessness Hypokinesia/Akinesia; Agitation Seizures (convulsions) Rigidity Akathisia Confusion Fatigue Insomnia | 39 19 7 6; 6; 4; 4; 4; 4; 3† 3 3 3 2 2
Cardiovascular Tachycardia Hypotension Hypertension | 25† 9 4
Gastrointestinal Constipation Nausea Abdominal Discomfort/Heartburn Nausea/Vomiting Vomiting Diarrhea | 14 5 4 3 3 2
Urogenital Urinary Abnormalities | 2
Autonomic Nervous System Salivation Sweating Dry Mouth Visual Disturbances | 31 6 6 5
Skin Rash | 2
Hemic/Lymphatic Leukopenia/Decreased WBC/Neutropenia | 3
Miscellaneous Fever Weight Gain | 5 4
† Rate based on population of approximately 1700 exposed during premarket clinical evaluation of clozapine.

Table 11 summarizes the most commonly reported adverse reactions (>10% of the clozapine or olanzapine group) in the InterSePT™Study. This was an adequate and well-controlled, two-year study evaluating the efficacy of clozapine relative to olanzapine in reducing the risk of suicidal behavior in patients with schizophrenia or schizoaffective disorder. The rates are not adjusted for duration of exposure.

Table 11: Incidence of Adverse Reactions in Patients Treated with Clozapine or Olanzapine in the InterSePT™ Study (≥10% in the clozapine or olanzapine group)

Adverse Reactions | Clozapine N=479 % Reporting | Olanzapine N=477 % Reporting
Salivary hypersecretion | 48% | 6%
Somnolence | 46% | 25%
Weight increased | 31% | 56%
Dizziness (excluding vertigo) | 27% | 12%
Constipation | 25% | 10%
Insomnia | 20% | 33%
Nausea | 17% | 10%
Vomiting | 17% | 9%
Dyspepsia | 14% | 8%

Dystonia

Class effect: Symptoms of dystonia, prolonged abnormal contractions of muscle groups, may occur in susceptible individuals during the first few days of treatment. Dystonic symptoms include: spasm of the neck muscles, sometimes progressing to tightness of the throat, swallowing difficulty, difficulty breathing, and/or protrusion of the tongue. While these symptoms can occur at low doses, they occur more frequently and with greater severity with high potency and at higher doses of first generation antipsychotic drugs. An elevated risk of acute dystonia is observed in males and younger age groups.

6.2 Postmarketing Experience

The following adverse reactions have been identified during post-approval use of clozapine. Because these reactions are reported voluntarily from a population of uncertain size, it is not always possible to reliably estimate their frequency or establish a causal relationship to drug exposure.

Central Nervous System

Delirium, EEG abnormal, myoclonus, paresthesia, possible cataplexy, status epilepticus, obsessive compulsive symptoms, and post-discontinuation cholinergic rebound adverse reactions.

Cardiovascular System

Atrial or ventricular fibrillation, ventricular tachycardia, palpitations, QT interval prolongation, Torsades de Pointes, mitral valve incompetence associated with clozapine-related cardiomyopathy, myocardial infarction, cardiac arrest, myocarditis, pericarditis, and periorbital edema.

Endocrine System

Pseudopheochromocytoma.

Gastrointestinal System

Acute pancreatitis, dysphagia, salivary gland swelling, megacolon, fecal incontinence, and intestinal ischemia, infarction, perforation, ulceration or necrosis.

Hepatobiliary System

Cholestasis, hepatitis, jaundice, hepatotoxicity, hepatic steatosis, hepatic necrosis, hepatic fibrosis, hepatic cirrhosis, liver injury (hepatic, cholestatic, and mixed), and liver failure.

Immune System Disorders

Angioedema, leukocytoclastic vasculitis.

Urogenital System

Acute interstitial nephritis, nocturnal enuresis, priapism, renal failure and retrograde ejaculation.

Skin and Subcutaneous Tissue Disorders

Hypersensitivity reactions: photosensitivity, vasculitis, erythema multiforme, skin pigmentation disorder, and Stevens-Johnson Syndrome.

Musculoskeletal System and Connective Tissue Disorders

Myasthenic syndrome, rhabdomyolysis, and systemic lupus erythematosus.

Respiratory System

Aspiration, pleural effusion, pneumonia, lower respiratory tract infection, sleep apnea.

Hemic and Lymphatic System

Mild, moderate, or severe leukopenia, agranulocytosis, granulocytopenia, WBC decreased, deep vein thrombosis, elevated hemoglobin/hematocrit, erythrocyte sedimentation rate (ESR) increased, sepsis, thrombocytosis, and thrombocytopenia.

Vision Disorders

Narrow-angle glaucoma.

Miscellaneous

Creatine phosphokinase elevation, hyperuricemia, hyponatremia, and weight loss.

7 DRUG INTERACTIONS

7.1 Potential for Other Drugs to Affect VERSACLOZ

Clozapine is a substrate for many cytochrome P450 isozymes, in particular CYP1A2, CYP3A4, and CYP2D6. Use caution when administering VERSACLOZ concomitantly with drugs that are inducers or inhibitors of these enzymes.

CYP1A2 Inhibitors

Concomitant use of VERSACLOZ and CYP1A2 inhibitors can increase plasma levels of clozapine, potentially resulting in adverse reactions. Reduce the VERSACLOZ dose to one third of the original dose when VERSACLOZ is coadministered with strong CYP1A2 inhibitors (e.g., fluvoxamine, ciprofloxacin, or enoxacin). The VERSACLOZ dose should be increased to the original dose when coadministration of strong CYP1A2 inhibitors is discontinued [see Dosage and Administration (2.8), Clinical Pharmacology (12.3)].

Moderate or weak CYP1A2 inhibitors include oral contraceptives and caffeine. Monitor patients closely when VERSACLOZ is coadministered with these inhibitors. Consider reducing the VERSACLOZ dosage if necessary [see Dosage and Administration (2.8)] .

CYP2D6 and CYP3A4 Inhibitors

Concomitant treatment with VERSACLOZ and CYP2D6 or CYP3A4 inhibitors (e.g., cimetidine, escitalopram, erythromycin, paroxetine, bupropion, fluoxetine, quinidine, duloxetine, terbinafine, or sertraline) can increase clozapine levels and lead to adverse reactions [see Clinical Pharmacology (12.3)] . Use caution and monitor patients closely when using such inhibitors. Consider reducing the VERSACLOZ dose [see Dosage and Administration (2.8)] .

CYP1A2 and CYP3A4 Inducers

Concomitant treatment with drugs that induce CYP1A2 or CYP3A4 can decrease the plasma concentration of clozapine, resulting in decreased effectiveness of VERSACLOZ. Tobacco smoke is a moderate inducer of CYP1A2. Strong CYP3A4 inducers include carbamazepine, phenytoin, St. John’s wort, and rifampin. It may be necessary to increase the VERSACLOZ dose if used concomitantly with inducers of these enzymes. However, concomitant use of VERSACLOZ and strong CYP3A4 inducers is not recommended [see Dosage and Administration (2.8)].

Consider reducing the VERSACLOZ dosage when discontinuing coadministered enzyme inducers, because discontinuation of inducers can result in increased clozapine plasma levels and an increased risk of adverse reactions [see Dosage and Administration (2.8)].
Anticholinergic DrugsConcomitant treatment with clozapine and other drugs with anticholinergic activity (e.g., benztropine, cyclobenzaprine, diphenhydramine) can increase the risk for anticholinergic toxicity and severe gastrointestinal adverse reactions related to hypomotility. Avoid concomitant use of VERSACLOZ with anticholinergic drugs when possible [see Warnings and Precautions (5.7, 5.15)].

Drugs that Cause QT Interval Prolongation

Use caution when administering concomitant medications that prolong the QT interval or inhibit the metabolism of VERSACLOZ. Drugs that cause QT prolongation include: specific antipsychotics (e.g., ziprasidone, iloperidone, chlorpromazine, thioridazine, mesoridazine, droperidol, and pimozide), specific antibiotics (e.g., erythromycin, gatifloxacin, moxifloxacin, sparfloxacin), Class 1A antiarrhythmics (e.g., quinidine, procainamide) or Class III antiarrhythmics (e.g., amiodarone, sotalol), and others (e.g., pentamidine, levomethadyl acetate, methadone, halofantrine, mefloquine, dolasetron mesylate, probucol or tacrolimus) [see Warnings and Precautions (5.9)].

7.2 Potential for VERSACLOZ to Affect Other Drugs

Concomitant use of VERSACLOZ with other drugs metabolized by CYP2D6 can increase levels of these CYP2D6 substrates. Use caution when coadministering VERSACLOZ with other drugs that are metabolized by CYP2D6. It may be necessary to use lower doses of such drugs than usually prescribed. Such drugs include specific antidepressants, phenothiazines, carbamazepine, and Type 1C antiarrhythmics (e.g., propafenone, flecainide, and encainide).

8 USE IN SPECIFIC POPULATIONS

8.1 Pregnancy

Pregnancy Exposure Registry

There is a pregnancy exposure registry that monitors pregnancy outcomes in women exposed to atypical antipsychotics, including VERSACLOZ, during pregnancy. Health care providers are encouraged to advise patients to register by contacting the National Pregnancy Registry for Atypical Antipsychotics at 1-866-961-2388 or visiting http://womensmental health.org/clinical-and-research-programs/pregnancyregistry/.

Risk Summary

Neonates exposed to antipsychotic drugs, including VERSACLOZ, during the third trimester are at risk for extrapyramidal and/or withdrawal symptoms following delivery (see Clinical Considerations). Available data from published epidemiologic studies over decades of use with clozapine during pregnancy have not established a drug-associated risk of major birth defects, miscarriage, or adverse maternal or fetal outcomes. (see Data) . There are risks to the mother associated with untreated schizophrenia and with exposure to antipsychotics, including VERSACLOZ, during pregnancy (see Clinical Considerations). In animal reproduction studies, no adverse developmental effects were observed when clozapine was administered orally to pregnant rats or rabbits during the period of organogenesis, or to pregnant rats during pregnancy and lactation, at doses up to approximately 0.4 and 0.9 times the maximum recommended human dose (MRHD) of 900 mg/day, for rats and rabbits respectively, based on mg/m^2body surface area (see Data) .

The background risk of major birth defects and miscarriage for the indicated populations is unknown. All pregnancies have a background risk of birth defects, loss, or other adverse outcomes. In the U.S. general population, the estimated background risk of major birth defects and miscarriage in clinically recognized pregnancies is 2 to 4% and 15 to 20%, respectively.
Clinical Considerations

Disease-associated maternal and/or embryo/fetal risk

There is a risk to the mother from untreated schizophrenia, including increased risk of relapse, hospitalization, and suicide. Schizophrenia is associated with increased adverse perinatal outcomes, including preterm birth. It is not known if this is a direct result of the illness or other comorbid factors.
Fetal/Neonatal adverse reactions

Extrapyramidal and/or withdrawal symptoms, including agitation, hypertonia, hypotonia, tremor, somnolence, respiratory distress, and feeding disorder have been reported in neonates who have been exposed to antipsychotic drugs, including VERSACLOZ, during the third trimester of pregnancy. These symptoms have varied in severity. Monitor neonates for extrapyramidal and/or withdrawal symptoms and manage symptoms appropriately. Some neonates recovered within hours or days without specific treatment; others required prolonged hospitalization.

Data

Human Data

Published data from observational studies, birth registries, and case reports on the use of atypical antipsychotics do not report a clear association with antipsychotics and major birth defects. A retrospective cohort study from a Medicaid database of 9258 women exposed to antipsychotics during pregnancy did not indicate an overall increased risk for major birth defects.
Animal Data

In embryofetal developmental studies, clozapine had no effects on maternal parameters, litter sizes, or fetal parameters when administered orally to pregnant rats and rabbits during the period of organogenesis at doses up to 0.4 and 0.9 times, respectively, the MRHD of 900 mg/day on a mg/m^2body surface area basis.

In peri/postnatal developmental studies, pregnant female rats were administered clozapine over the last third of pregnancy and until day 21 postpartum. Observations were made on fetuses at birth and during the postnatal period; the offspring were allowed to reach sexual maturity and mated. Clozapine caused a decrease in maternal body weight but had no effects on litter size or body weights of either F1 or F2 generations at doses up to 0.4 times the MRHD of 900 mg/day on a mg/m^2body surface area basis.

8.2 Lactation

Risk Summary

Clozapine is present in human milk. There are reports of sedation and a report of agranulocytosis in an infant exposed to clozapine through human milk (see Clinical Considerations). There is no information on the effects of clozapine on milk production.
The developmental and health benefits of breastfeeding should be considered along with the mother’s clinical need for VERSACLOZ and any potential adverse effects on the breastfed-child from VERSACLOZ or from the underlying maternal condition.
Clinical Considerations

Infants exposed to VERSACLOZ should be monitored for excess sedation and neutropenia.

8.4 Pediatric Use

Safety and effectiveness in pediatric patients have not been established.

8.5 Geriatric Use

There have not been sufficient numbers of geriatric patients in clinical studies utilizing VERSACLOZ to determine whether those over 65 years of age differ from younger subjects in their response to VERSACLOZ.

Orthostatic hypotension and tachycardia can occur with clozapine treatment [see Boxed Warning and Warnings and Precautions (5.2)]. Elderly patients, particularly those with compromised cardiovascular functioning, may be more susceptible to these effects.

Elderly patients may be particularly susceptible to the anticholinergic effects of clozapine, such as urinary retention and constipation [see Warnings and Precautions (5.15)].

Carefully select VERSACLOZ doses in elderly patients, taking into consideration their greater frequency of decreased hepatic, renal, or cardiac function, as well as other concomitant disease and other drug therapy. Clinical experience suggests that the prevalence of tardive dyskinesia appears to be highest among the elderly; especially elderly women [see Warnings and Precautions (5.17)].

8.6 Patients with Renal or Hepatic Impairment

Dose reduction may be necessary in patients with significant impairment of renal or hepatic function. Clozapine concentrations may be increased in these patients, because clozapine is almost completely metabolized and then excreted [see Dosage and Administration (2.9), Clinical Pharmacology (12.3)].

8.7 CYP2D6 Poor Metabolizers

Dose reduction may be necessary in patients who are CYP2D6 poor metabolizers. Clozapine concentrations may be increased in these patients, because clozapine is almost completely metabolized and then excreted [see Dosage and Administration (2.8), Clinical Pharmacology (12.3)].

10 OVERDOSAGE

10.1 Overdosage Experience

The most commonly reported signs and symptoms associated with clozapine overdose are: sedation, delirium, coma, tachycardia, hypotension, respiratory depression or failure, and hypersalivation. There are reports of aspiration pneumonia, cardiac arrhythmias, and seizure. Fatal overdoses have been reported with clozapine, generally at doses above 2500 mg. There have also been reports of patients recovering from overdoses well in excess of 4 g.

10.2 Management of Overdosage

There are no specific antidotes for VERSACLOZ. Establish and maintain an airway; ensure adequate oxygenation and ventilation. Monitor cardiac status and vital signs. Use general symptomatic and supportive measures. Consider the possibility of multiple-drug involvement.

Contact a Certified Poison Control Center for the most up to date information on the management of overdosage (1-800-222-1222).

11 DESCRIPTION

VERSACLOZ, an atypical antipsychotic drug, is a tricyclic dibenzodiazepine derivative, 8-chloro-11-(4-methyl-1-piperazinyl)-5 H-dibenzo[ b,e][1,4]diazepine.

The is:

VERSACLOZ is available as a free-flowing yellow suspension. Each mL contains 50 mg of clozapine.

The active component of VERSACLOZ is clozapine. The remaining components are glycerin, sorbitol (crystallizing), sodium dihydrogen phosphate dihydrate, xanthan gum, sodium methylparaben, sodium propylparaben, povidone, water, and sodium hydroxide to adjust to a pH range of 6.5 – 7.0.

12 CLINICAL PHARMACOLOGY

12.1 Mechanism of Action

The mechanism of action of clozapine is unknown. However, it has been proposed that the therapeutic efficacy of clozapine in schizophrenia is mediated through antagonism of the dopamine type 2 (D2) and the serotonin type 2A (5-HT2A) receptors. VERSACLOZ also acts as an antagonist at adrenergic, cholinergic, histaminergic and other dopaminergic and serotonergic receptors.

12.2 Pharmacodynamics

Clozapine demonstrated binding affinity to the following receptors: histamine H1(Ki1.1 nM), adrenergic α1A(Ki1.6 nM), serotonin 5-HT6(Ki4 nM), serotonin 5-HT2A(Ki5.4 nM), muscarinic M1(Ki6.2 nM), serotonin 5-HT7(Ki6.3 nM), serotonin 5-HT2C(Ki9.4 nM), dopamine D4(Ki24 nM), adrenergic α2A(Ki90 nM), serotonin 5-HT3 (Ki 95 nM), serotonin 5-HT1A(Ki120 nM), dopamine D2(Ki160 nM), dopamine D1(Ki270 nM), dopamine D5(Ki454 nM), and dopamine D3(Ki555 nM).

Clozapine causes little or no prolactin elevation.

Clinical electroencephalogram (EEG) studies demonstrated that clozapine increases delta and theta activity and slows dominant alpha frequencies. Enhanced synchronization occurs. Sharp wave activity and spike and wave complexes may also develop. Patients have reported an intensification of dream activity during clozapine therapy. REM sleep was found to be increased to 85% of the total sleep time. In these patients, the onset of REM sleep occurred almost immediately after falling asleep.

12.3 Pharmacokinetics

Absorption

In man, clozapine tablets (25 mg and 100 mg) are equally bioavailable relative to a clozapine solution. VERSACLOZ Oral Suspension is bioequivalent to clozapine marketed tablets.

Following oral administration of 100 mg to 800 mg VERSACLOZ, once daily, the average steady-state peak plasma concentration was 275 ng/mL (range: 105 - 723 ng/mL), occurring at the average of 2.2 hours (range: 1 - 3.5 hours) after dosing. The average minimum concentration at steady-state was 75 ng/mL (range: 11 - 198 ng/mL).

When VERSACLOZ was administered after a high fat meal there was no effect on the AUCssor Cmin, ss, however Cmaxwas reduced about 20%, and there was a slight delay in Tmaxof 0.5 hour from a median Tmax of 2.0 hours under fasted conditions to 2.5 hours under fed conditions. The decrease in Cmaxis not considered clinically relevant. Therefore VERSACLOZ may be taken without regard to meals.

Distribution

Clozapine is approximately 97% bound to serum proteins. The interaction between clozapine and other highly protein-bound drugs has not been fully evaluated but may be important [see Drug Interactions (7)].

Metabolism and Excretion

VERSACLOZ is almost completely metabolized prior to excretion, and only trace amounts of unchanged drug are detected in the urine and feces. VERSACLOZ is a substrate for many cytochrome P450 isozymes, in particular CYP1A2, CYP2D6, and CYP3A4. Approximately 50% of the administered dose is excreted in the urine and 30% in the feces. The demethylated, hydroxylated, and N-oxide derivatives are components in both urine and feces. Pharmacological testing has shown the desmethyl metabolite (norclozapine) to have only limited activity, while the hydroxylated and N-oxide derivatives were inactive. The mean elimination half-life of clozapine after a single 75 mg dose was 8 hours (range: 4-12 hours), compared to a mean elimination half-life of 12 hours (range: 4-66 hours), after achieving steady-state with 100 mg twice daily dosing.

A comparison of single-dose and multiple-dose administration of clozapine demonstrated that the elimination half-life increased significantly after multiple dosing relative to that after single-dose administration, suggesting the possibility of concentration-dependent pharmacokinetics. However, at steady-state, approximately dose-proportional changes with respect to AUC (area under the curve), peak, and minimum clozapine plasma concentrations were observed after administration of 37.5, 75, and 150 mg twice daily.

Drug-Drug Interaction Studies

Fluvoxamine

A pharmacokinetic study was conducted in 16 patients with schizophrenia who received clozapine under steady-state conditions. After coadministration of fluvoxamine for 14 days, mean trough concentrations of clozapine and its metabolites, N-desmethylclozapine and clozapine N-oxide, were elevated about three-fold compared to baseline steady-state concentrations.

Paroxetine, Fluoxetine, and Sertraline

In a study of patients with schizophrenia (n=14) who received clozapine under steady-state conditions, coadministration of paroxetine produced only minor changes in the levels of clozapine and its metabolites. However, other published reports describe modest elevations (less than two-fold) of clozapine and metabolite concentrations when clozapine was taken with paroxetine, fluoxetine, and sertraline.

Specific Populations

Renal or Hepatic Impairment

No specific pharmacokinetic studies were conducted to investigate the effects of renal or hepatic impairment on the pharmacokinetics of clozapine. Higher clozapine plasma concentrations are likely in patients with significant renal or hepatic impairment when given usual doses.

CYP2D6 Poor Metabolizers

A subset (3%–10%) of the population has reduced activity of CYP2D6 (CYP2D6 poor metabolizers). These individuals may develop higher than expected plasma concentrations of clozapine when given usual doses.

Patients with Pneumonia and other Inflammatory Conditions

Published case reports describe examples where pneumonia or other inflammatory- conditions may increase clozapine concentrations. The clinical significance, the impact of treatments to modulate this inflammation, and mechanism of this potential increase in clozapine concentrations have not been fully characterized but may involve reduced cytochrome P450 1A2 activity.

13 NONCLINICAL TOXICOLOGY

13.1 Carcinogenesis, Mutagenesis, Impairment of Fertility

Carcinogenesis

No carcinogenic potential was demonstrated in long-term studies in mice and rats at doses up to 0.3 times and 0.4 times, respectively, the maximum recommended human dose (MRHD) of 900 mg/day on a mg/m^2body surface area basis.

Mutagenesis

Clozapine was not genotoxic when tested in the following gene mutation and chromosomal aberration tests: the bacterial Ames test, the in vitromammalian V79 in Chinese hamster cells, the in vitrounscheduled DNA synthesis in rat hepatocytes, or the in vivomicronucleus assay in mice.

Impairment of Fertility

Clozapine had no effect on any parameters of fertility, pregnancy, fetal weight, or postnatal development when administered orally to male rats 70 days before mating and to female rats for 14 days before mating at doses up to 0.4 times the MRHD of 900 mg/day on a mg/m^2body surface area basis.

14 CLINICAL STUDIES

14.1 Treatment-Resistant Schizophrenia

The efficacy of clozapine in treatment-resistant schizophrenia was established in a multicenter, randomized, double-blind, active-controlled (chlorpromazine) study in patients with a DSM-III diagnosis of schizophrenia who had inadequate responses to at least 3 different antipsychotics (from at least 2 different chemical classes) during the preceding 5 years. The antipsychotic trials must have been judged adequate; the antipsychotic dosages must have been equivalent to or greater than 1000 mg per day of chlorpromazine for a period of at least 6 weeks, each without significant reduction of symptoms. There must have been no period of good functioning within the preceding 5 years. Patients must have had a baseline score of at least 45 on the investigator-rated Brief Psychiatric Rating Scale (BPRS). On the 18-item BPRS, 1 indicates the absence of symptoms, and 7 indicates severe symptoms; the maximum potential total BPRS score is 126. At baseline, the mean BPRS score was 61. In addition, patients must have had a score of at least 4 on at least two of the following four individual BPRS items: conceptual disorganization, suspiciousness, hallucinatory behavior, and unusual thought content. Patients must have had a Clinical Global Impressions – Severity Scale score of at least 4 (moderately ill).

In the prospective, lead-in phase of the trial, all patients (N=305) initially received single-blind treatment with haloperidol (the mean dose was 61 mg per day) for 6 weeks. More than 80% of patients completed the 6-week trial. Patients with an inadequate response to haloperidol (n=268) were randomized to double-blind treatment with clozapine (N=126) or chlorpromazine (N=142). The maximum daily clozapine dose was 900 mg; the mean daily dose was >600 mg). The maximum daily chlorpromazine dose was 1800 mg; the mean daily dose was >1200 mg.

The primary endpoint was treatment response, predefined as a decrease in BPRS score of at least 20% and either (1) a CGI-S score of <3 (mildly ill), or (2) a BPRS score of <35, at the end of 6 weeks of treatment. Approximately 88% of patients from the clozapine and chlorpromazine groups completed the 6-week trial. At the end of six weeks, 30% of the clozapine group responded to treatment, and 4% of the chlorpromazine group responded to treatment. The difference was statistically significant (p<0.001). The mean change in total BPRS score was -16 and -5 in the clozapine and chlorpromazine group, respectively; the mean change in the 4 key BPRS item scores was -5 and -2 in the clozapine and chlorpromazine group, respectively; and the mean change in CGI-S score was -1.2 and -0.4, in the clozapine and chlorpromazine group, respectively. These changes in the clozapine group were statistically significantly greater than in the chlorpromazine group (p<0.001 in each analysis).

14.2 Recurrent Suicidal Behavior in Schizophrenia or Schizoaffective Disorder

he effectiveness of clozapine in reducing the risk of recurrent suicidal behavior was assessed in the International Suicide Prevention Trial (InterSePT™, a trademark of Novartis Pharmaceuticals Corporation). This was a prospective, randomized, open-label, active-controlled, multicenter, international, parallel-group comparison of clozapine (Clozaril®) versus olanzapine (Zyprexa®, a registered trademark of Eli Lilly and Company) in 956 patients with schizophrenia or schizoaffective disorder (DSM-IV) who were judged to be at risk for recurrent suicidal behavior. Only about one-fourth of these patients (27%) were considered resistant to standard antipsychotic drug treatment. To enter the trial, patients must have met one of the following criteria:

- They had attempted suicide within the three years prior to their baseline evaluation.
- They had been hospitalized to prevent a suicide attempt within the three years prior to their baseline evaluation.
- They demonstrated moderate-to-severe suicidal ideation with a depressive component within one week prior to their baseline evaluation.
- They demonstrated moderate-to-severe suicidal ideation accompanied by command hallucinations to do self-harm within one week prior to their baseline evaluation.

Dosing regimens for each treatment group were determined by individual investigators and were individualized by patient. Dosing was flexible, with a dose range of 200–900 mg/day for clozapine and 5–20 mg/day for olanzapine. For the 956 patients who received clozapine or olanzapine in this study, there was extensive use of concomitant psychotropics: 84% with antipsychotics, 65% with anxiolytics, 53% with antidepressants, and 28% with mood stabilizers. There was significantly greater use of concomitant psychotropic medications among the patients in the olanzapine group.

The primary efficacy measure was time to (1) a significant suicide attempt, including a completed suicide; (2) hospitalization due to imminent suicide risk, including increased level of surveillance for suicidality for patients already hospitalized; or (3) worsening of suicidality severity as demonstrated by “much worsening” or “very much worsening” from baseline in the Clinical Global Impression of Severity of Suicidality as assessed by the Blinded Psychiatrist (CGI-SS-BP) scale. A determination of whether or not a reported event met criterion 1 or 2 above was made by the Suicide Monitoring Board (SMB), a group of experts blinded to patient data.

A total of 980 patients were randomized to the study and 956 received study medication. Sixty-two percent of the patients were diagnosed with schizophrenia, and the remainder (38%) were diagnosed with schizoaffective disorder. Only about one-fourth of the total patient population (27%) was identified as “treatment-resistant” at baseline. There were more males than females in the study (61% of all patients were male). The mean age of patients entering the study was 37 years of age (range: 18–69). Most patients were Caucasian (71%), 15% were Black, 1% were Asian, and 13% were classified as being of “other” races.

Patients treated with clozapine had a statistically significant longer delay in the time to recurrent suicidal behavior in comparison with olanzapine. This result should be interpreted only as evidence of the effectiveness of clozapine in delaying time to recurrent suicidal behavior and not a demonstration of the superior efficacy of clozapine over olanzapine.

The probability of experiencing (1) a significant suicide attempt, including a completed suicide, or (2) hospitalization because of imminent suicide risk, including increased level of surveillance for suicidality for patients already hospitalized, was lower for clozapine patients than for olanzapine patients at Week 104: clozapine 24% versus olanzapine 32%; 95% CI of the difference: 2%, 14% (Figure 1).

Figure 1. Cumulative Probability of a Significant Suicide Attempt or Hospitalization to Prevent Suicide in Patients with Schizophrenia or Schizoaffective Disorder at High Risk of Suicidality

16 HOW SUPPLIED/STORAGE AND HANDLING

16.1 How Supplied

Oral Suspension

Free-flowing, yellow suspension (50 mg/mL) in amber bottle containing 100 mL. Each box contains 1 x 1 mL oral syringe, 1 x 9 mL oral syringe and 1 bottle adaptor.

NDC No. 52817-601-38

16.2 Storage and Handling

Store VERSACLOZ at room temperature between 20°C to 25°C (68°F to 77°F); excursion permitted between 15°C to 30°C (59°F to 86°F) [see USP Controlled Room Temperature]. Do not refrigerate or freeze. Protect from light. Shake well for 10 seconds before use.

The suspension is stable for 100 days after initial bottle opening. Keep out of reach of children

17 PATIENT COUNSELING INFORMATION

Advise the patient to read the FDA-approved patient labeling (Medication Guide and Instructions for Use).

• Severe Neutropenia:
Instruct patients (and caregivers) [see Warnings and Precautions (5.1)]:

- About the risk of developing severe neutropenia and infection with VERSACLOZ treatment.

- To immediately report to their health care provider any symptom or sign of infection during VERSACLOZ treatment.

- About the importance of having frequent ANC testing.

• Orthostatic Hypotension, Bradycardia, and Syncope:Inform patients and caregivers about the risk of orthostatic hypotension and syncope, especially during the period of initial dose titration. Instruct them to strictly follow the clinician’s instructions for dosage and administration [see Dosage and Administration (2.2., 2.7)]. Advise patients to consult their clinician immediately if they feel faint, lose consciousness or have signs or symptoms suggestive of bradycardia or arrhythmia [see Warnings and Precautions (5.2)].
• Falls:Inform patients of the risk of falls, which may lead to fractures or other injuries [see Warnings and Precautions (5.3)].
• Seizures:Inform patients and caregivers about the significant risk of seizure during VERSACLOZ treatment. Caution them about driving and any other potentially hazardous activity while taking VERSACLOZ [see Warnings and Precautions (5.4)].
• Gastrointestinal Hypomotility with Severe Complications:Educate patients and caregivers on the risks, prevention, and treatment of clozapine-induced constipation, including medications to avoid when possible (e.g., drugs with anticholinergic activity). Encourage appropriate hydration, physical activity, and fiber intake and emphasize that prompt attention and treatment to the development of constipation or other gastrointestinal symptoms is critical in preventing severe complications. Advise patients and caregivers to contact their health care provider if they experience symptoms of constipation (e.g., difficulty passing stools, incomplete passage of stool, decreased bowel movement frequency) or other symptoms associated with gastrointestinal hypomotility (e.g., nausea, abdominal distension or pain, vomiting) [see Warnings and Precautions (5.7), Drug Interactions (7.1)].
• QT Interval Prolongation:Advise patients to consult their clinician immediately if they feel faint, lose consciousness, or have signs or symptoms suggestive of arrhythmia. Instruct patients to not take VERSACLOZ with other drugs that cause QT interval prolongation. Instruct patients to inform their clinicians that they are taking VERSACLOZ before any new drug [see Warnings and Precautions (5.9) and Drug Interactions (7.1)].
• Metabolic Changes (hyperglycemia and diabetes mellitus, dyslipidemia, weight gain):Educate patients and caregivers about the risk of metabolic changes and the need for specific monitoring. The risks include hyperglycemia and diabetes mellitus, dyslipidemia, weight gain, and cardiovascular reactions. Educate patients and caregivers about the symptoms of hyperglycemia (high blood sugar) and diabetes mellitus (e.g., polydipsia, polyuria, polyphagia, and weakness). Monitor all patients for these symptoms. Patients who are diagnosed with diabetes or have risk factors for diabetes (obesity, family history of diabetes) should have their fasting blood glucose monitored before beginning treatment and periodically during treatment. Patients who develop symptoms of hyperglycemia should have assessments of fasting glucose. Clinical monitoring of weight is recommended [see Warnings and Precautions (5.10)].
• Interference with Cognitive and Motor Performance:Because VERSACLOZ may have the potential to impair judgment, thinking, or motor skills, patients should be cautioned about operating hazardous machinery, including automobiles, until they are reasonably certain that VERSACLOZ therapy does not affect them adversely [see Warnings and Precautions (5.16)].
• Hepatotoxicity:Instruct patients to immediately report to their physician any symptoms or signs of potential liver injury (e.g. fatigue, malaise, anorexia, nausea, jaundice, bilirubinemia, coagulopathy, and hepatic encephalopathy). [see Warnings and Precautions (5.12)].
• Missed Doses and Re-Initiating Treatment:Inform patients and caregivers that if the patient misses taking VERSACLOZ for 1 day or more, they should not restart their medication at the same dosage but should contact their physician for dosing instructions [see Dosage and Administration (2.7) and Warnings and Precautions (5.1, 5.2)].
• Pregnancy:Advise pregnant women to notify their healthcare provider if they become pregnant or intend to become pregnant during treatment with VERSACLOZ. Advise patients that VERSACLOZ may cause extrapyramidal and/or withdrawal symptoms (agitation, hypertonia, hypotonia, tremor, somnolence, respiratory distress, and feeding disorder) in a neonate. Advise patients that there is a pregnancy exposure registry that monitors pregnancy outcomes in women exposed to VERSACLOZ during pregnancy [see Use in Specific Populations (8.1)].
• Lactation:Advise breastfeeding women using VERSACLOZ to monitor infants for excess sedation and to seek medical care if they notice this sign. Inform breastfeeding women using VERSACLOZ that their healthcare provider will monitor infants for neutropenia [see Use in Specific Populations (8.2)].
• Concomitant Medication:Advise patients to inform their healthcare provider if they are taking, or plan to take, any prescription or over-the-counter drugs; there is a potential for significant drug-drug interactions [see Dosage and Administration (2.8), Drug Interactions (7.1)].
• Patient Instructions for Use:Educate the patient and caregiver about the Patient Instructions for Use if VERSACLOZ will be administered at home. Discuss the specific steps for administering the prescribed dose using the oral syringe. [see Dosage and Administration (2.3)].

Distributed by:
TruPharma, LLC
Tampa, FL 33609

U.S. Patent No. 8057811
VERSACLOZ is a registered trademark of Douglas Pharmaceuticals Limited in New Zealand and other countries.

311653
Revised: June 2025

Patient Information

MEDICATION GUIDE

VERSACLOZ (VER sa kloz)

(clozapine)

oral suspension

What is the most important information I should know about VERSACLOZ? VERSACLOZ can cause serious side effects, including:

- Severe neutropenia (low white blood cell (WBC) counts) that can lead to serious infections and death.Your healthcare provider will do WBC blood tests before starting treatment with VERSACLOZ and weekly for the first 6 months. After your first 6 months of treatment, your healthcare provider will determine how frequent you will have blood tests. If you have symptoms of severe neutropenia or an infection, your healthcare provider will do more frequent WBC blood test(s) to check if VERSACLOZ is causing your symptoms and may send you to see a blood specialist (hematologist). Tell your health care provider right away if you have any of the following symptoms or signs of neutropenia or infection:

- feel like you have the flu

- wounds that take a long time heal

- fever or chills

- skin, throat, vaginal, urinary tract, or lung infection

- feel extremely tired or weak

- pain or burning while peeing

- sores or ulcers inside your mouth, gums, or on your skin

- unusual vaginal discharge or itching

- sores or pain in or around your rectal area

- abdominal pain or bloating

- Orthostatic hypotension (decreased blood pressure), bradycardia (slow heart rate), or syncope (fainting) that can lead to death. You feel lightheaded or faint when you rise too quickly from a sitting or lying position. Tell your healthcare provider right away if you feel dizzy or pass out.
- Seizures.See “What should I avoid while taking VERSACLOZ?”

- Myocarditis (heart muscle inflammation), pericarditis (inflammation of outer layer of the heart) and cardiomyopathy (heart muscle weakness) that can lead to death.Symptoms of myocarditis, pericarditis, and cardiomyopathy include:

- chest pain

- flu-like symptoms

- fast heartbeat or palpitations

- feel tired or faint

- shortness of breath

- swollen legs, ankles, or fee

- fever

- Increased risk of death in elderly people with dementia-related psychosis.Medicines likeVERSACLOZ can increase the risk of death in elderly people who have lost touch with reality (psychosis) due to confusion and dementia.

VERSACLOZ is not for treatment of elderly people with dementia-related psychosis.

What is VERSACLOZ?

VERSACLOZ is a prescription antipsychotic medicine used to treat people:

- Who are severely ill with schizophrenia not helped by other schizophrenia medicines
- With schizophrenia or schizoaffective disorder who have been suicidal and may be at risk of suicidal behavior again

It is not known if VERSACLOZ is safe and effective in children.

Who should not take VERSACLOZ?

Do not take VERSACLOZ if you:

are allergic to clozapine or any of the ingredients in VERSACLOZ. See the end of this Medication Guide for a complete list of ingredients in VERSACLOZ.

Before taking VERSACLOZ, tell your healthcare provider about all your medical conditions, including if you:

- have or have had heart problems or a family history of heart problems including heart attack, heart failure, abnormal heart rhythm or long QT syndrome, or stroke
- have or have had low or high blood pressure
- have or have had kidney or liver problems
- have or have had seizures (convulsions)
- have or have had stomach or intestinal problems including constipation, slow emptying of your stomach, or diarrhea
- have or have had low levels of potassium or magnesium in your blood
- have or have had diabetes or high blood sugar in you or your family
- have or have had high levels of total cholesterol, “bad” cholesterol (LDL-C), or triglycerides, or low levels of “good” cholesterol (HDL-C)
- have increased pressure in your eyes (glaucoma), an enlarged prostate, or problems passing urine
- have or have had uncontrolled movements of your tongue, face, mouth, or jaw (tardive dyskinesia)
- smoke tobacco
- plan to stop smoking tobacco while taking VERSACLOZ
- use products containing caffeine
- are pregnant or plan to become pregnant. Talk to your healthcare provider if you become pregnant while taking VERSACLOZ.
  - If you become pregnant while receiving VERSACLOZ, talk to your healthcare provider about registering with the National Pregnancy Registry for Atypical Antipsychotics. You can register by calling 1-866-961-2388 or go to http://womensmentalhealth.org/clinical-and-research- programs/pregnancyregistry/
- are breast feeding or plan to breast feed. VERSACLOZ can pass into your breast milk and may harm your baby. Talk to your healthcare provider about the best way to feed your baby if you take VERSACLOZ.

Tell your healthcare provider about all the medicines you take, including

prescription and over-the-counter medicines, vitamins, and herbal supplements.

- VERSACLOZ and other medicines may affect each other causing side effects.
- Your healthcare provider can tell you if it is safe to take VERSACLOZ with your other medicines. Do not start or stop any medicines while taking VERSACLOZ without talking to your healthcare provider first.
- Know the medicines you take. Keep a list of them to show your healthcare provider and pharmacist when you get a new medicine.

How should I take VERSACLOZ?

- Take VERSACLOZ exactly as your healthcare provider tells you to take it. Do notchange your dose or stop taking VERSACLOZ unless your healthcare provider tells you to. Talk to your healthcare provider or pharmacist if you are not sure how to take VERSACLOZ.
- Take VERSACLOZ with or without food.
- If your healthcare provider decides that you can take VERSACLOZ at home, you should receive training on the correct way to take VERSACLOZ. Do nottry to take VERSACLOZ yourself until you have been shown how to take VERSACLOZ.
- See the detailed Instructions for Useat the end of this Medication Guide for information on how to take VERSACLOZ.
- If you miss taking VERSACLOZ for 1 day or more, call your healthcare provider right away. Do not take 2 doses at the same time unless your healthcare provider tells you to.
- If you take too much (overdose) VERSACLOZ, call your healthcare provider or the Poison Help line at 1-800-222-1222 or go to the nearest hospital emergency room right away.

Symptoms of VERSACLOZ overdose can include:

- feeling sleepy

- fast or irregular heartbeat

- having a lot of saliva in your mouth

- confusion

- low blood pressure

- seizures

- coma

- shallow or difficult breathing

What should I avoid while taking VERSACLOZ?

- You should not drink alcohol while taking VERSACLOZ because it can increase your chances of getting serious side effects.
- Do not drive, operate machinery, swim, climb, or do dangerous activities until you know how VERSACLOZ affects you.

What are the possible side effects of VERSACLOZ?

VERSACLOZ may cause serious side effects, including:

- See "What is the most important information I should know about VERSACLOZ?"
- falls.VERSACLOZ may make you sleepy, dizzy, may cause a decrease in your blood pressure when changing positions, and can slow your thinking and motor skills which may lead to falls that can cause fractures or other injuries.
- slow emptying of your stomach and intestines (decreased gastric motility). Severe constipation and bowel problems can happen and can lead to hospitalization, surgery, and death.You may not feel or be aware of constipation symptoms. Your healthcare provider will examine you for possible bowel problems. Tell your healthcare provider if you get any signs and symptoms of decreased gastrointestinal motility during treatment during treatment with VERSACLOZ, including:

- having bowel movements less than normal

- stomach bloating or pain

- hard or dry stools

- nausea or vomiting

- difficulty in passing gas

Staying well hydrated, increasing physical activity, and taking fiber during treatment with VERSACLOZ can help prevent constipation and other bowel problems. Your healthcare provider may prescribe medicines to prevent severe problems.

- high count of a certain white blood cell (eosinophilia).VERSACLOZ can cause a high count of eosinophils in some people and can be serious. This is a different risk than the risk of VERSACLOZ causing an abnormally low white blood cell count (neutropenia). Your health care provider may send you to see an internal medicine specialist (internist) or blood specialist (hematologist). Tell your healthcare provider right away if you have any of these symptoms:

- feeling very tired or weak

- coughing and wheezing

- fever

- nausea, vomiting, or diarrhea

- rash

- night sweats

- swelling

- confusion

- joint pain

- difficulty swallowing

- serious heart rhythm problems (QTc Interval Prolongation) that can cause death.Your healthcare provider will do a physical exam and may obtain blood tests and an electrocardiogram before starting you on treatment with VERSACLOZ. Tell your healthcare provider right away if you have any of these symptoms:
  - passing out or feeling like you will pass out
  - dizziness
  - feeling as if your heart is pounding or missing beats
- problems with your metabolism such as:
  - high blood sugar (hyperglycemia) or diabetes. Increases in blood sugar can happen in some people who take VERSACLOZ. Extremely high blood sugar can lead to coma and death. If you have diabetes or risk factors for diabetes (such as being overweight), your health care provider should check your blood sugar before you start VERSACLOZ and during treatment. Tell your healthcare provider if you have any of these symptoms of high blood sugar while taking VERSACLOZ:

- feel very thirsty

- feel very hungry

- feel sick to your stomach

- need to urinate more than usual

- feel weak or tired

- feel confused, or your breath smells fruity

-
  - increased fat levels (cholesterol and triglycerides) in your blood (dyslipidemia).Your healthcare provider should check the fat levels in your blood before you start and during treatment with VERSACLOZ.
  - weight gain.You and your healthcare provider should check your weight regularly.

- neuroleptic malignant syndrome (NMS).NMS is a rare but serious condition that can lead to death and must be treated in a hospital. Tell your healthcare provider right away if you become severely ill and have any of these symptoms:

- high fever

- confusion

- increased sweating

- stiff muscles

- changes in breathing, heartbeat, and blood pressure

- liver problems.VERSACLOZ can cause serious life-threatening liver problems that can lead to death. Tell your healthcare provider right away if you have any of these symptoms:

- feeling tired

- nausea and vomiting

- pain on the right side of your stomach (abdomen)

- loss of appetite

- yellowing of your skin or whites of your eyes

- elevated bilirubin levels

- fever.Some people may have a fever while they take VERSACLOZ. If you have a fever, your healthcare provider will do blood tests to check for neutropenia or an infection. Your healthcare provider may also send you to see a blood specialist (hematologist). Tell your healthcare provider if you have a fever.
- blood clot in your lung (pulmonary embolism) or in the veins of your legs (deep vein thrombosis).Get emergency help right away if you have symptoms of a blood clot including:
  - chest pain and shortness of breath
  - swelling or pain in your leg, ankle or foot
  - warm feeling in the skin of your affected leg
  - changes in your skin color such as turning pale or blue
- a problem that includes dry mouth, increased sweating, increased pulse rate, constipation, and urinary retention (anticholinergic toxicity).
- problems thinking clearly and moving your body. See “What should I avoid while taking VERSACLOZ?”
- uncontrolled movements of your tongue, face, mouth, or jaw (tardive dyskinesia) .Tardive dyskinesia may not go away, even if you stop VERSACLOZ. Tardive dyskinesia may also start after you stop taking VERSACLOZ.
- stroke (cerebrovascular problems) in elderly people with dementia-related psychosis that can lead to death.

The most common side effects of VERSACLOZ include:

- sleepiness or drowsiness

- headache

- dizziness

- shaking movements (tremors)

- heart and blood vessel problems

- low blood pressure

- fast heartbeat

- having a lot of saliva in your mouth

- passing out (syncope)

- dry mouth

- increased sweating

- constipation and nausea

- vision problems

- fever

- These are not all the possible side effects of VERSACLOZ.
- Your healthcare provider may lower your dose or temporarily or permanently stop treatment with VERSACLOZ if you have certain symptoms or if your WBC count is low.
- Tell your healthcare provider if you have any side effect that bothers you or that does not go away.

You may report side effects to FDA at 1-800-FDA-1088.

How should I store VERSACLOZ?

- Store VERSACLOZ at room temperature between 68°F to 77°F (20°C to 25°C).
- Do not refrigerate VERSACLOZ.
- Do not freeze VERSACLOZ.
- Keep the VERSACLOZ bottle in the carton to protect it from light.
- Throw away (discard) any unused VERSACLOZ oral suspension remaining after 100 days of first opening the bottle.

Keep VERSACLOZ and all medicines out of the reach of children.

General information about the safe and effective use of VERSACLOZ

Medicines are sometimes prescribed for purposes other than those listed in a Medication Guide. Do not use VERSACLOZ for a condition for which it was not prescribed. Do not give VERSACLOZ to other people, even if they have the same symptoms that you have. It may harm them. You can ask your healthcare provider (including pharmacist) for information about VERSACLOZ that is written for healthcare professionals.

What are the ingredients in VERSACLOZ?

Active ingredient:clozapine

Inactive ingredients:glycerin, sorbitol (crystallizing), sodium dihydrogen phosphate dihydrate, xanthan gum, sodium methylparaben, sodium propylparaben, povidone, water, and sodium hydroxide

Distributed by:

TruPharma, LLC

Tampa, FL 33609

For optional information, go to www.VERSACLOZ.com or call 1-800-520-5538.

This Medication Guide has been approved by the U.S. Food and Drug Administration.

Issued: June 2025

Instructions for Use

VERSACLOZ®(VER sa kloz)

(clozapine)

oral suspension

Supplies you will need to take your VERSACLOZ dose:

- VERSACLOZ®oral Suspension bottle
- a bottle neck adaptor
- the correct oral syringe to measure your dose

ο If your dose is 1 mL (50 mg) or less, use the smaller 1 mL oral syringe.
ο If your dose is more than 1 mL (50 mg),use the larger 9 mL oral syringe.

Disposal of your oral syringe, empty VERSACLOZ bottle and bottle neck adaptor:

Place the cap back on the empty VERSACLOZ bottle before you throw it away. The oral syringe, empty bottle and bottle neck adaptor should be placed in your household trash when you finish your bottle of VERSACLOZ. The oral syringe should not be shared with other people or used for medicines other than VERSACLOZ.

Distributed by:

TruPharma, LLC

Tampa, FL 33609

This Patient Information and the Instructions for Use have been approved by the U.S. Food and Drug Administration.

311653 Revised: June 2025

PACKAGE LABEL PRINCIPAL DISPLAY PANEL-Container Label

Rx Only

Versacloz®

(clozapine) Oral Suspension

50 mg/mL

Cotainer Label

Carton Label